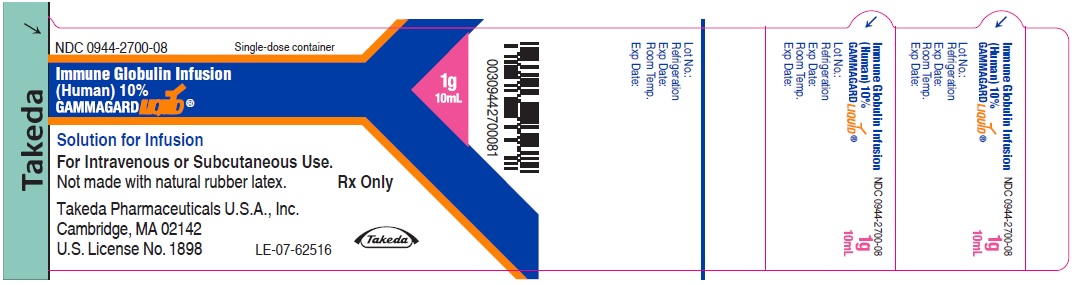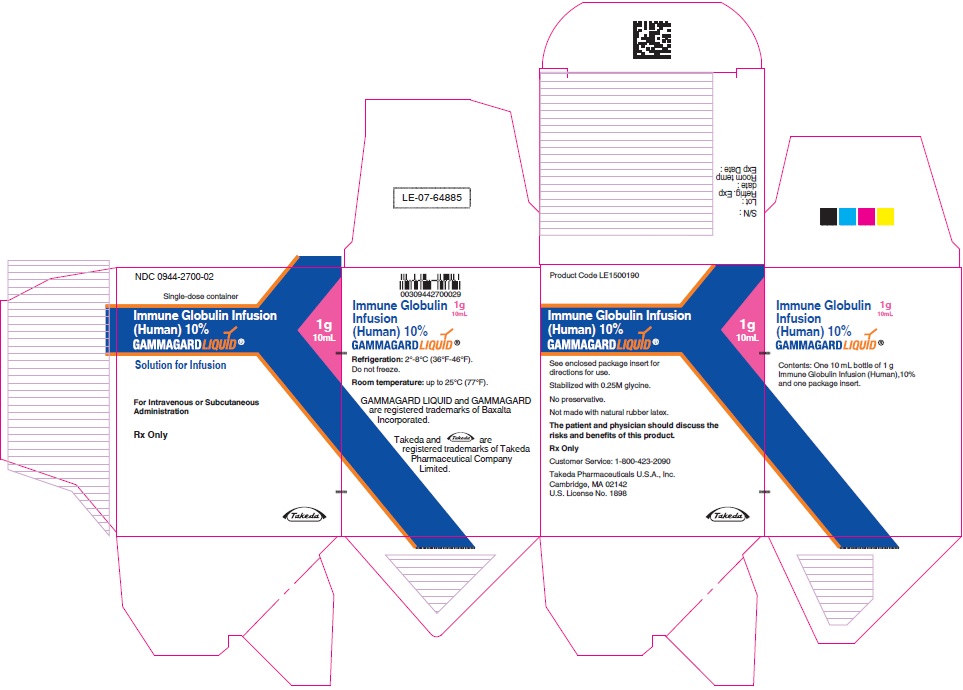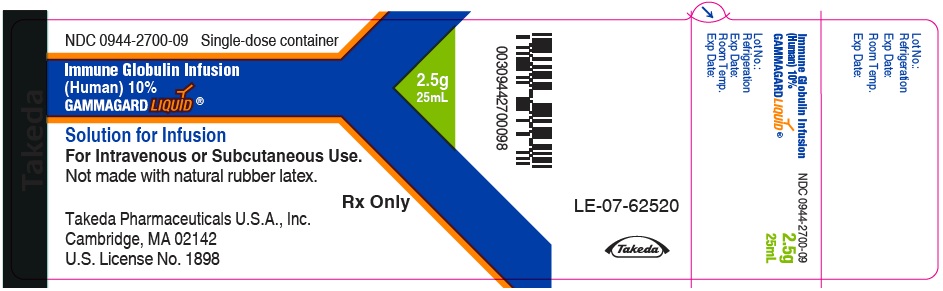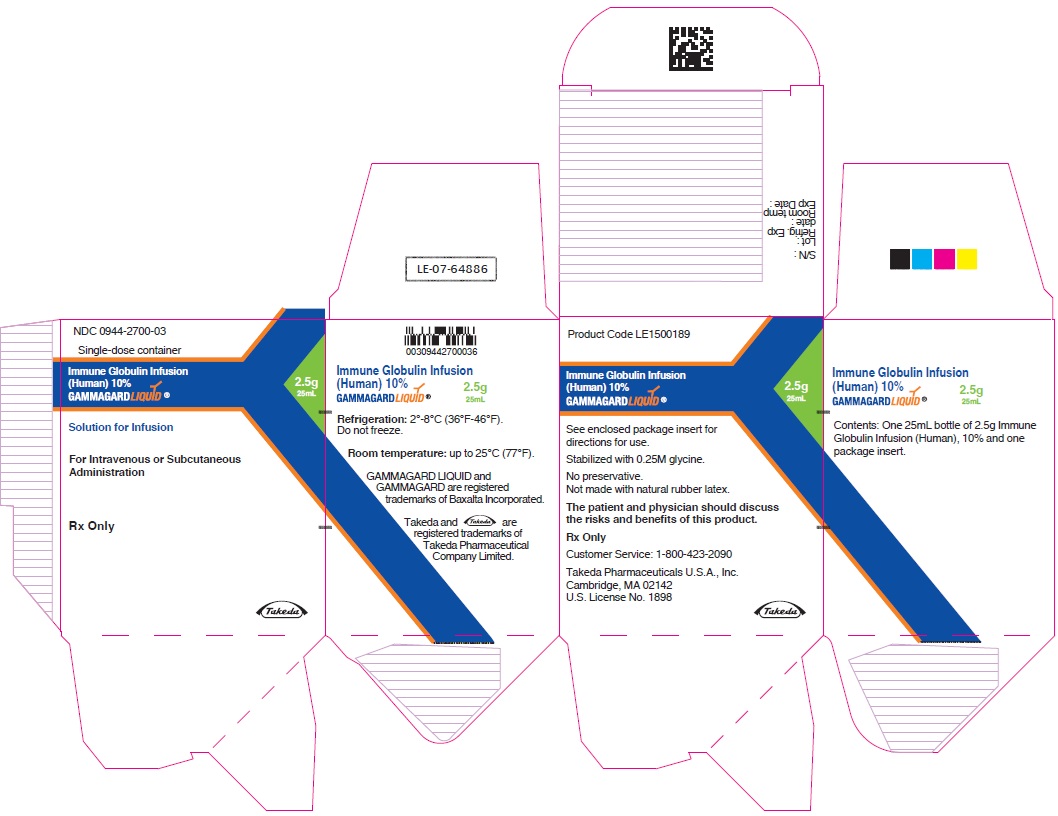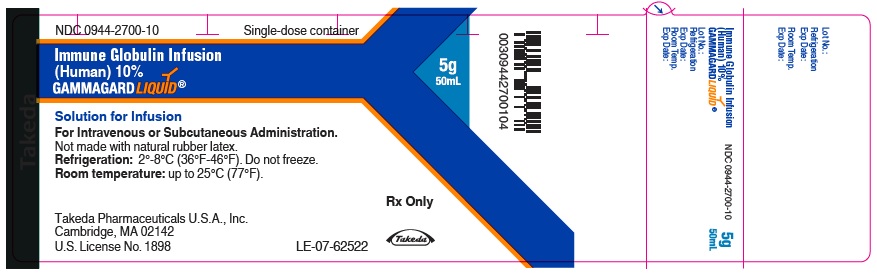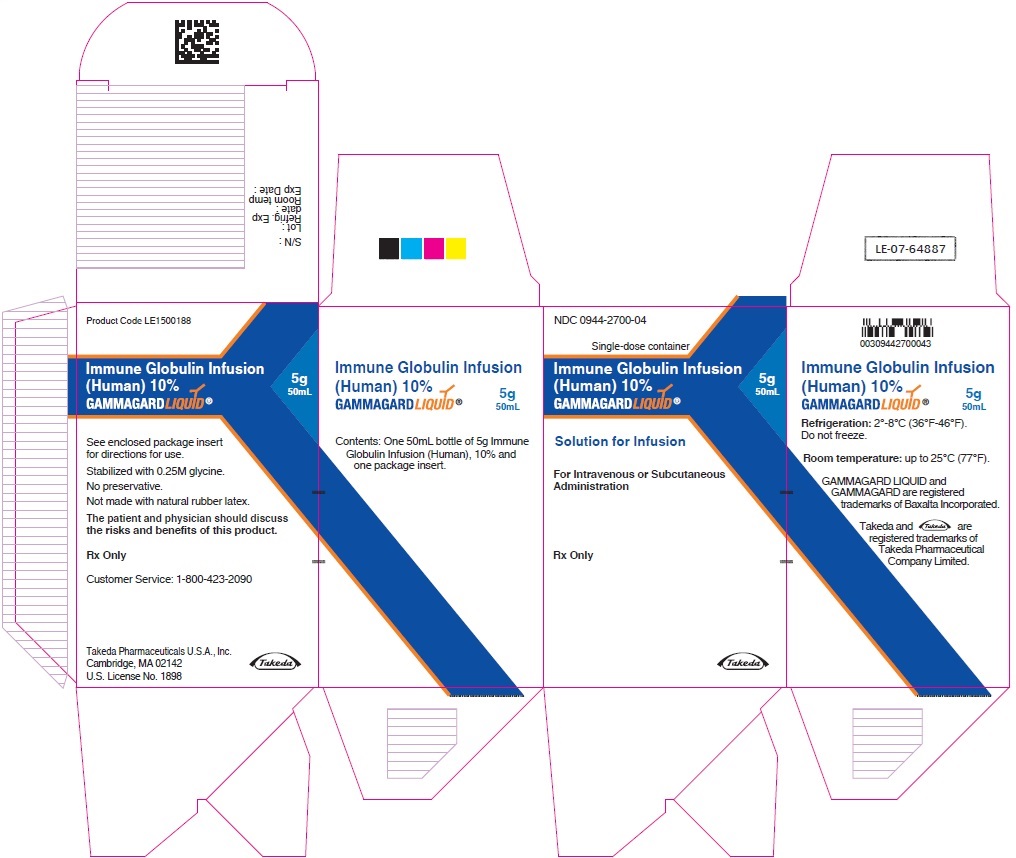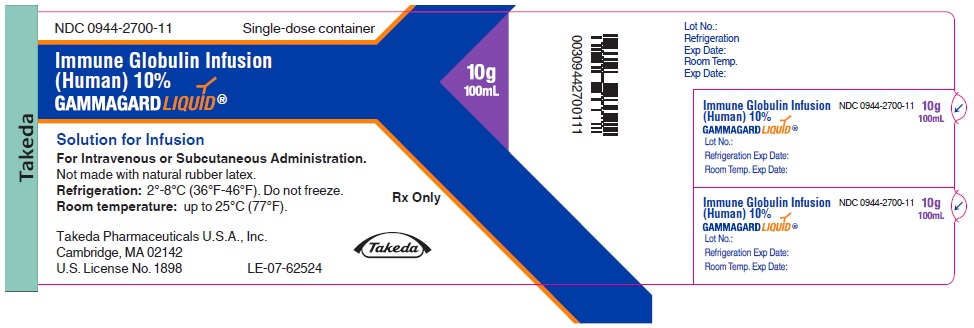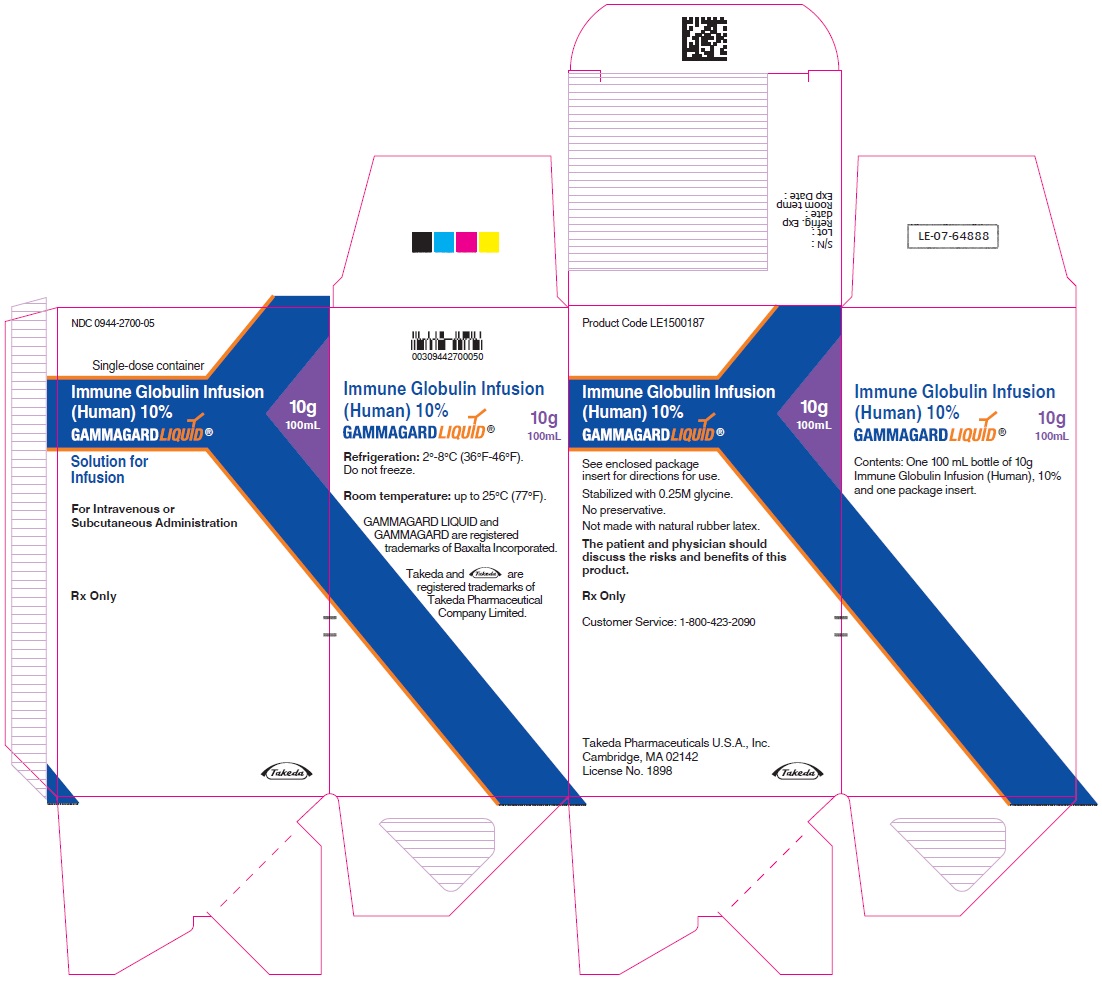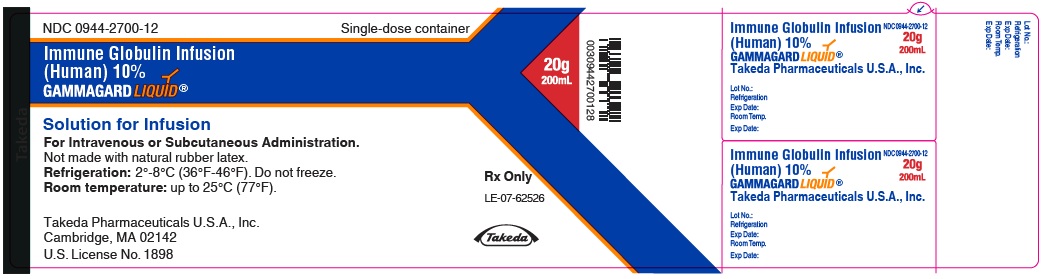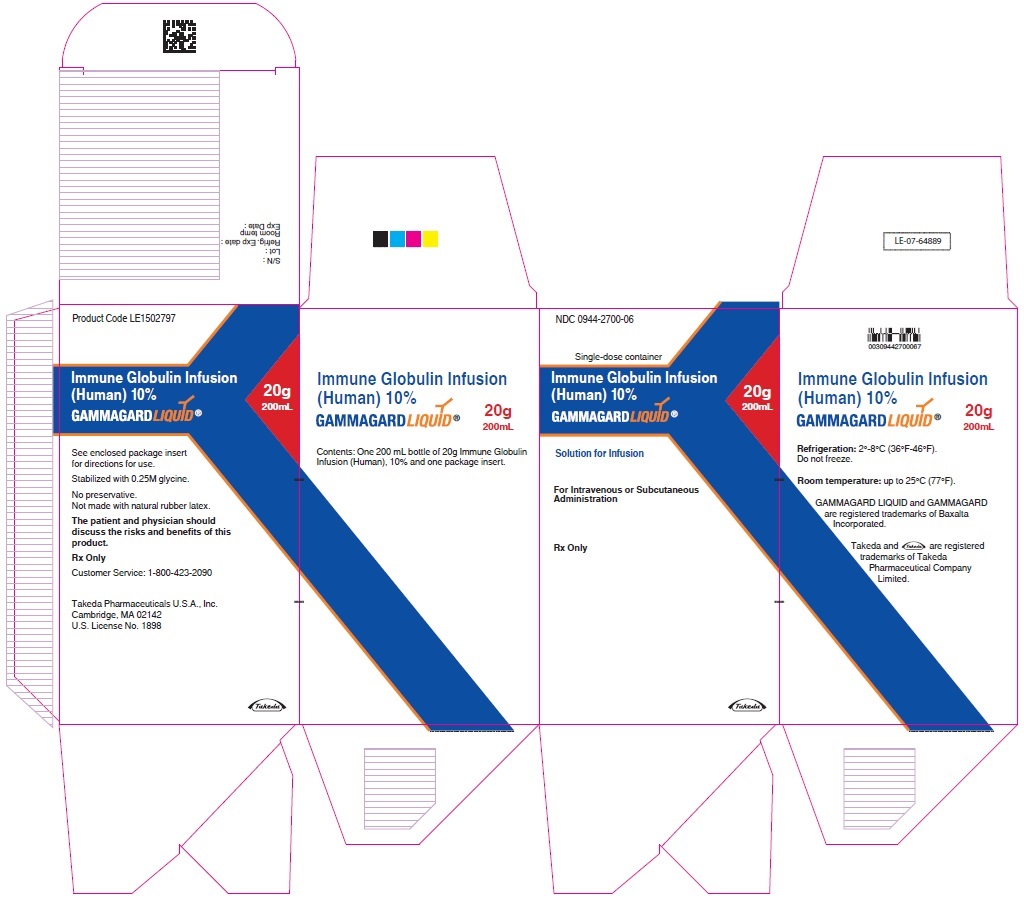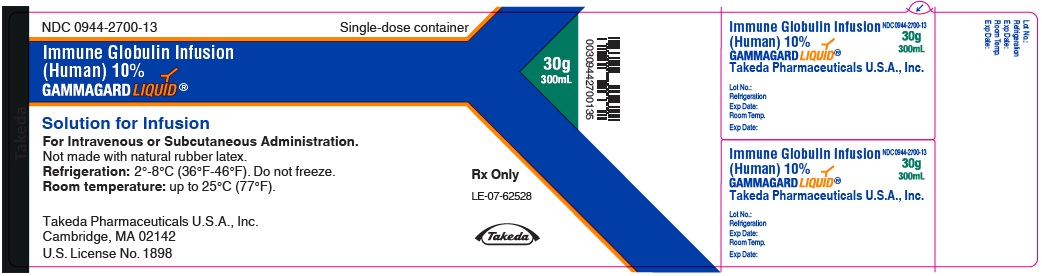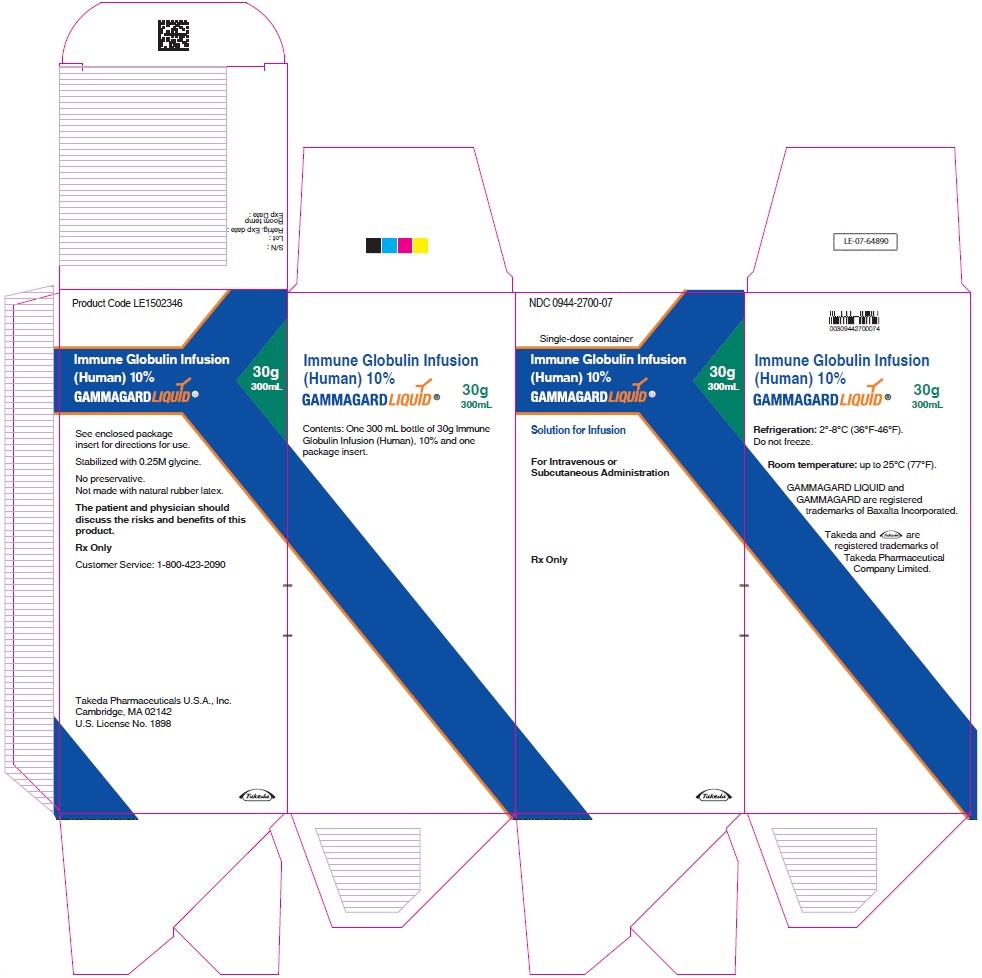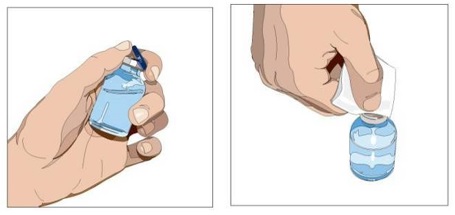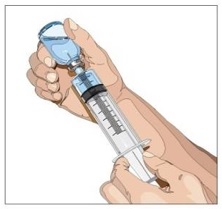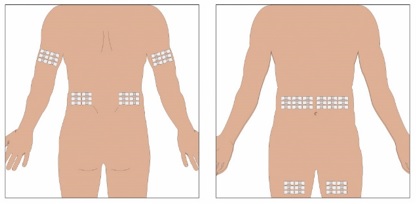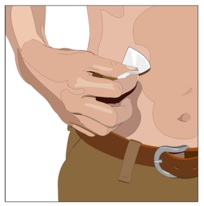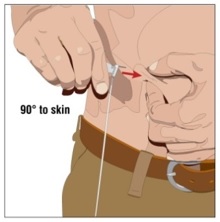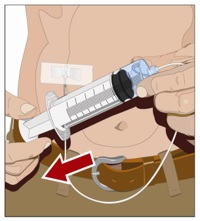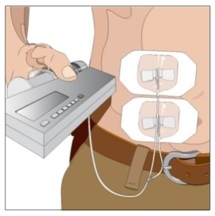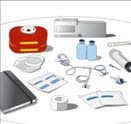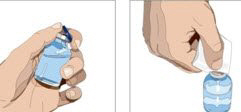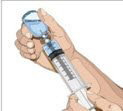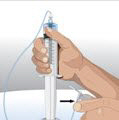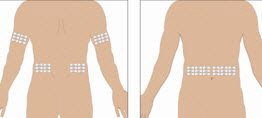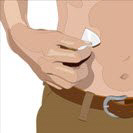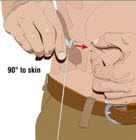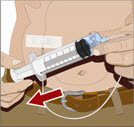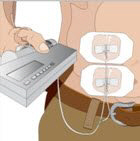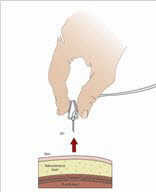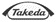 DRUG LABEL: GAMMAGARD Liquid
NDC: 0944-2700 | Form: INJECTION, SOLUTION
Manufacturer: Takeda Pharmaceuticals America, Inc.
Category: other | Type: PLASMA DERIVATIVE
Date: 20251210

ACTIVE INGREDIENTS: HUMAN IMMUNOGLOBULIN G 100 mg/1 mL
INACTIVE INGREDIENTS: GLYCINE

HIGHLIGHTS OF PRESCRIBING INFORMATION

These highlights do not include all the information needed to use GAMMAGARD LIQUID® safely and effectively. See full prescribing information for GAMMAGARD LIQUID.
GAMMAGARD LIQUID®, Immune Globulin Infusion (Human), 10% Solution, for intravenous and subcutaneous administration
Initial U.S. Approval: 2005

WARNING: THROMBOSIS, RENAL DYSFUNCTION and ACUTE RENAL FAILURE

See full prescribing information for complete boxed warning.

- Thrombosis may occur with immune globulin products, including GAMMAGARD LIQUID. Risk factors may include advanced age, prolonged immobilization, hypercoagulable conditions, history of venous or arterial thrombosis, use of estrogens, indwelling vascular catheters, hyperviscosity and cardiovascular risk factors. (5.4)
- Renal dysfunction, acute renal failure, osmotic nephrosis, and death may occur in predisposed patients with immune globulin intravenous (IGIV) products including GAMMAGARD LIQUID. Renal dysfunction and acute failure occur more commonly with IGIV products containing sucrose. GAMMAGARD LIQUID does not contain sucrose. (5.2)
- For patients at risk of thrombosis, administer GAMMAGARD LIQUID at the minimum dose and infusion rate practicable. Ensure adequate hydration in patients before administration. Monitor for signs and symptoms of thrombosis and assess blood viscosity in patients at risk of hyperviscosity. (5.4)

RECENT MAJOR CHANGES

▪ Indications and Usage (1.3) | 1/2024
▪ Dosage and Administration (2.3) | 1/2024

1 INDICATIONS AND USAGE

GAMMAGARD LIQUID is an immune globulin infusion (human) indicated as a:

- Replacement therapy for primary humoral immunodeficiency (PI) in adult and pediatric patients two years of age or older. (1.1)
- Maintenance therapy to improve muscle strength and disability in adult patients with Multifocal Motor Neuropathy (MMN). (1.2)
- Therapy to improve neuromuscular disability and impairment in adult patients with Chronic Inflammatory Demyelinating Polyneuropathy (CIDP). (1.3)

Limitations of Use:

- Safety and effectiveness of GAMMAGARD LIQUID has not been studied in immunoglobulin-naïve patients with CIDP. (1.3)
- GAMAGARD LIQUID maintenance therapy in CIDP has not been studied beyond 6 months (1.3)

2 DOSAGE AND ADMINISTRATION

PI: Intravenous (IV) (2.1)

Dose | Initial Infusion Rate | Maintenance Infusion Rate
300 to 600 milligram (mg)/kg every 3 to 4 weeks based on clinical response | 0.5milliliter (mL)/kg/hr (0.8 mg/kg/min) for 30 minutes | Increase every 30minutes (if tolerated) up to 5 mL/kg/hr (8 mg/kg/min)

Subcutaneous (SC) (2.1)

Dose | Initial Infusion Rate | Maintenance Infusion Rate
Initial Dose is 1.37 × previous intravenous dose divided by # of weeks between intravenous doses. Maintenance dose is based on clinical response and target IgG trough level. | 40 kg BW and greater: 30 mL/site at 20 mL/hr/site Under 40 kg BW: 20 mL/site at 15 mL/hr/site | 40 kg BW and greater: 30 mL/site at 20 to 30 mL/hr/site Under 40 kg BW: 20 mL/site at 15 to 20 mL/hr/site

MMN: Intravenous (IV) (2.2)

Dose | Initial Infusion Rate | Maintenance Infusion Rate
Dose range 0.5 to 2.4 gram/kg/month based on clinical response | 0.5mL/kg/hr (0.8 mg/kg/min) | Infusion rate may be advanced if tolerated to 5.4 mL/kg/hr (9 mg/kg/min)

CIDP: Intravenous (IV) (2.3)

Dose | Initial Infusion Rate | Maintenance Infusion Rate
Induction dose is 2 g/kg in divided doses over 2 to 5 consecutive days, followed by maintenance infusions. Maintenance dose is 1 g/kg in divided doses over 1 to 4 consecutive days, every 3 weeks. | 0.5 mL/kg/hr (0.8 mg/kg/min) | Infusion rate may be increased if tolerated up to 5.4 mL/kg/hr (9 mg/kg/min)

- Ensure patients with pre-existing renal insufficiency are not volume depleted; discontinue GAMMAGARD LIQUID if renal function deteriorates. (2.5, 5.2)
- For patients at risk of renal dysfunction or thrombotic events, administer GAMMAGARD LIQUID at minimum infusion rate practicable. (2.5, 5.2, 5.4)

3 DOSAGE FORMS AND STRENGTHS

Aqueous solution containing 10% IgG (100 mg/mL) (3)

4 CONTRAINDICATIONS

- Anaphylactic or severe systemic hypersensitivity reactions to Immune Globulin (Human) (4)
- IgA deficient patients with antibodies against IgA and a history of hypersensitivity (4)

5 WARNINGS AND PRECAUTIONS

- IgA deficient patients with antibodies to IgA are at greater risk of developing severe hypersensitivity and anaphylactic reaction. (5.1)
- Monitor renal function, including blood urea nitrogen, serum creatinine, and urine output in patients at risk of acute renal failure. (5.2)
- Hyperproteinemia, increased serum viscosity and hyponatremia may occur. (5.3)
- Thrombosis may occur. Monitor for signs and symptoms of thrombosis and assess blood viscosity for those at risk for hyperviscosity. (5.4)
- Aseptic Meningitis Syndrome (AMS) may occur. (5.5)
- Hemolytic anemia can develop. Monitor for clinical signs and symptoms of hemolysis and hemolytic anemia. (5.6)
- Monitor patients for pulmonary adverse reactions (transfusion-related acute lung injury, TRALI). (5.7)
- GAMMAGARD LIQUID is made from human blood, it may carry a risk of transmitting infectious agents, e.g., viruses, the variant Creutzfeldt-Jakob disease (vCJD) agent, and theoretically, the Creutzfeldt-Jakob disease agent (5.8)

6 ADVERSE REACTIONS

The most common adverse reactions observed in ≥5% of subjects were:

PI: Intravenous Administration: Headache, fatigue, pyrexia, nausea, chills, rigors, pain in extremity, diarrhea, migraine, dizziness, vomiting, cough, urticaria, asthma, pharyngolaryngeal pain, rash, arthralgia, myalgia, oedema peripheral, pruritus, and cardiac murmur. (6.1)

Subcutaneous Administration: Infusion site (local) event, headache, fatigue, heart rate increased, pyrexia, abdominal pain upper, nausea, vomiting, asthma, blood pressure systolic increased, diarrhea, ear pain, aphthous stomatitis, migraine, oropharyngeal pain, and pain in extremity. (6.1)

MMN: Headache, chest discomfort, muscle spasms, muscular weakness, nausea, oropharyngeal pain, and pain in extremity. (6.1)

CIDP: Headache, pyrexia anemia, leukopenia, neutropenia, illness, blood creatinine increased, dizziness, migraine, somnolence, tremor, nasal dryness, abdominal pain upper, vomiting, chills, nasopharyngitis, and pain in extremity. (6.1)

To report SUSPECTED ADVERSE REACTIONS, contact Takeda Pharmaceuticals U.S.A., Inc. at 1-877-TAKEDA-7 (1-877-825-3327) or FDA at 1-800-FDA-1088 or www.fda.gov/medwatch.

7 DRUG INTERACTIONS

Passive transfer of antibodies may transiently interfere with immune responses to live virus vaccines, such as measles, mumps, rubella, and varicella. (7)

8 USE IN SPECIFIC POPULATIONS

Geriatric: In patients over age 65 or in any patient at risk of developing renal insufficiency, do not exceed the recommended dose. Infuse GAMMAGARD LIQUID at the minimum infusion rate practicable. (8.5)

FULL PRESCRIBING INFORMATION

WARNING: THROMBOSIS, RENAL DYSFUNCTION and ACUTE RENAL FAILURE

- Thrombosis may occur with immune globulin products, including GAMMAGARD LIQUID. Risk factors may include advanced age, prolonged immobilization, hypercoagulable conditions, history of venous or arterial thrombosis, use of estrogens, indwelling vascular catheters, hyperviscosity and cardiovascular risk factors. Thrombosis may occur in the absence of known risk factors [see Warnings and Precautions (5.4), Patient Counseling Information (17)].
- Renal dysfunction, acute renal failure, osmotic nephrosis, and death may occur in predisposed patients with immune globulin intravenous (IGIV) products. Patients predisposed to renal dysfunction include those with any degree of pre-existing renal insufficiency, diabetes mellitus, age greater than 65, volume depletion, sepsis, paraproteinemia, or patients receiving known nephrotoxic drugs. Renal dysfunction and acute renal failure occur more commonly in patients receiving IGIV products containing sucrose. GAMMAGARD LIQUID does not contain sucrose. [see Warnings and Precautions (5.2)
- For patients at risk of thrombosis, administer GAMMAGARD LIQUID at the minimum dose and infusion rate practicable. Ensure adequate hydration in patients before administration. Monitor for signs and symptoms of thrombosis and assess blood viscosity in patients at risk of hyperviscosity [see Dosage and Administration (2.3) and Warnings and Precautions (5.4)].

1 INDICATIONS AND USAGE

1.1 Primary Immunodeficiency (PI)

GAMMAGARD LIQUID is indicated as replacement therapy for primary humoral immunodeficiency (PI) in adult and pediatric patients two years of age or older. This includes, but is not limited to, common variable immunodeficiency (CVID), X-linked agammaglobulinemia, congenital agammaglobulinemia, Wiskott-Aldrich syndrome, and severe combined immunodeficiencies.^1,2

1.2 Multifocal Motor Neuropathy (MMN)

GAMMAGARD LIQUID is indicated as a maintenance therapy to improve muscle strength and disability in adult patients with Multifocal Motor Neuropathy (MMN).

1.3 Chronic Inflammatory Demyelinating Polyneuropathy (CIDP)

GAMMAGARD LIQUID is indicated as a therapy to improve neuromuscular disability and impairment in adult patients with Chronic Inflammatory Demyelinating Polyneuropathy (CIDP).

Limitation of Use

GAMMAGARD LIQUID has not been studied in immunoglobulin-naive patients with CIDP. GAMMAGARD LIQUID maintenance therapy in CIDP has not been studied for periods longer than 6 months. After responding during an initial treatment period, not all patients require indefinite maintenance therapy with GAMMAGARD LIQUID in order to remain free of CIDP symptoms. Individualize the duration of any treatment beyond 6 months based upon the patient’s response and demonstrated need for continued therapy.

2 DOSAGE AND ADMINISTRATION

2.1 Dosage for Primary Immunodeficiency

Intravenous Administration (IV)

Table 1: Recommended Dosage for Primary Immunodeficiency (Intravenous Administration)
Dose | Initial Infusion rate | Maintenance Infusion rate
300 to 600 milligram (mg)/kg every 3 to 4 weeks based on clinical response | 0.5 milliliter (mL)/kg/hr (0.8mg/kg/min) for 30 minutes | Increase every 30 minutes (if tolerated) up to 5 mL/kg/hr (8mg/kg/min)

Dose Adjustments

Adjust dose according to IgG levels and clinical response, as the frequency and dose of immune globulin may vary from patient to patient.

No randomized controlled clinical studies are available to determine an optimum trough serum IgG level for intravenous treatment. If a patient misses a dose, administer the missed dose as soon as possible, and then resume scheduled treatments every 3 or 4 weeks, as applicable.

Prior to switching from intravenous to subcutaneous treatment, obtain the patient's serum IgG trough level to guide subsequent dose adjustments. Start the initial subcutaneous dose approximately one week after the last intravenous infusion.

Dose Adjustments for Measles Exposure

If a patient has been exposed to measles, it may be prudent to administer an extra dose of GAMMAGARD LIQUID as soon as possible and within 6 days of exposure. A dose of 400 mg/kg should provide a serum level > 240 mIU/mL of measles antibodies for at least two weeks.

If a patient is at risk of future measles exposure and receives a dose of less than 530 mg/kg every 3 to 4 weeks, the dose should be increased to at least 530 mg/kg. This should provide a serum level of 240 mIU/mL of measles antibodies for at least 22 days after infusion.

Subcutaneous Administration (SC)

Table 2: Recommended Dosage for Primary Immunodeficiency (Subcutaneous Administration)
Dose | Initial Infusion rate | Maintenance Infusion rate
Initial dose is 1.37 × previous intravenous dose divided by # of weeks between intravenous doses. Maintenance dose is based on clinical response and target IgG trough level. | 40 kg BW and greater: 30 mL/site at 20 mL/hr/site. Under 40 kg BW: 20 mL/site at 15 mL/hr/site. | 40 kg BW and greater: 30 mL/site at 20 to 30 mL/hr/site. Under 40 kg BW: 20 mL/site at 15 to 20 mL/hr/site.

Dose Adjustments

Based on the results of clinical studies, the expected increase in serum IgG trough level during weekly subcutaneous treatment at the dose adjusted to provide a comparable AUC, is approximately 281 mg/dL higher than the last IgG trough level during prior stable intravenous treatment. To calculate the target trough IgG level for subcutaneous treatment, add 281 mg/dL to the IgG trough level obtained after the last intravenous treatment.

To guide dose adjustment, calculate the difference between the patient's target serum IgG trough level and the IgG trough level during subcutaneous treatment. Find this difference in the columns of Table 3 and the corresponding amount (in mL) by which to increase (or decrease) the weekly dose based on the patient's body weight. If the difference between measured and target trough levels is less than 100 mg/dL then no adjustment is necessary. However, the patient's clinical response should be the primary consideration in dose adjustment.

Table 3: Change in Weekly Dose of GAMMAGARD LIQUID for Intended IgG Trough Level Adjustment [Derived using a linear approximation to the nomogram method with a slope of 5.3 kg/dL.]
 | Difference between Measured and Target IgG Trough Levels
Body Weight | 100 mg/dL | 200 mg/dL | 300 mg/dL | 400 mg/dL
10 kg | 2 mL | 4 mL | 6 mL | 8 mL
20 kg | 4 mL | 8 mL | 11 mL | 15 mL
30 kg | 6 mL | 11 mL | 17 mL | 23 mL
40 kg | 8 mL | 15 mL | 23 mL | 30 mL
50 kg | 9 mL | 19 mL | 28 mL | 38 mL
60 kg | 11 mL | 23 mL | 34 mL | 45 mL
70 kg | 13 mL | 26 mL | 40 mL | 53 mL
80 kg | 15 mL | 30 mL | 45 mL | 60 mL
90 kg | 17 mL | 34 mL | 51 mL | 68 mL
100 kg | 19 mL | 38 mL | 57 mL | 75 mL
110 kg | 21 mL | 42 mL | 62 mL | 83 mL
120 kg | 23 mL | 45 mL | 68 mL | 91 mL
130 kg | 25 mL | 49 mL | 74 mL | 98 mL
140 kg | 26 mL | 53 mL | 79 mL | 106 mL

Example 1: A patient with a body weight of 80 kg has a measured IgG trough level of 800 mg/dL and the target trough level is 1000 mg/dL. The desired target trough level difference is 200 mg/dL (1000 mg/dL minus 800 mg/dL). The weekly dose of GAMMAGARD LIQUID should be increased by 30 mL (3.0 gm).

Example 2: A patient with a body weight of 60 kg has a measured IgG trough of 1000 mg/dL and the target trough level is 800 mg/dL. The desired target trough level difference is 200 mg/dL (800 mg/dL minus 1000 mg/dL). The weekly dose of GAMMAGARD LIQUID should be decreased by 23 mL (2.3 gm).

2.2 Dosage for Multifocal Motor Neuropathy

Intravenous Administration (IV)

Table 4: Recommended Dosage for Multifocal Motor Neuropathy
Dose | Initial Infusion rate | Maintenance Infusion rate
Dose range 0.5 to 2.4 gram/kg/month based on clinical response (14) | 0.5 mL/kg/hr (0.8 mg/kg/min) | Infusion rate may be increased if tolerated up to 5.4 mL/kg/hr (9 mg/kg/min)

Dose Adjustments

The dose may need to be adjusted to achieve the desired clinical response. In the clinical study, the dose ranged between 0.5 to 2.4 grams/kg/month. While receiving GAMMAGARD LIQUID, 9% of subjects in the clinical study experienced neurological decompensation that required an increase in dose. In order to avoid worsening of muscle weakness in patients, dose adjustment may be necessary.

2.3 Dosage for Chronic Inflammatory Demyelinating Polyneuropathy

Intravenous Administration (IV)

Table 5: Recommended Dosage for Chronic Inflammatory Demyelinating Polyneuropathy
Dose | Initial Infusion rate | Maintenance Infusion rate
Induction dose is 2 g/kg in divided doses over 2 to 5 consecutive days, followed by maintenance infusions. Maintenance dose is 1 g/kg in divided doses over 1 to 4 consecutive days, every 3 weeks. | 0.5 mL/kg/hr (0.8 mg/kg/min) | Infusion rate may be increased if tolerated up to 5.4 mL/kg/hr (9 mg/kg/min)

Dose Adjustments

The induction dose is 2 g/kg divided over 2 to 5 consecutive days, followed by 1 g/kg maintenance doses divided over 1 to 4 days consecutive days, every 3 weeks. The maintenance dose level and dosing interval of GAMMAGARD LIQUID treatment may be adjusted according to the clinical response.

The recommended initial infusion rate is 0.5 mL/kg/hr (0.8 mg/kg/min). If the infusion is well tolerated, the rate may be gradually increased to a maximum of 5.4 mL/kg/hr (9 mg/kg/min). [see Administration (2.5)].

For patients at risk of renal dysfunction or thromboembolic events, do not exceed the recommended dose. Infuse at the minimum intravenous infusion rate practicable [see Warnings and Precautions (5.2, 5.4) and Use In Specific Populations (8.5)].

2.4 Preparation and Handling

- Inspect the drug product visually for particulate matter and discoloration prior to administration. GAMMAGARD LIQUID is a clear or slightly opalescent, colorless or pale-yellow solution. Do not use if the solution is cloudy, turbid, or if it contains particulates.
- GAMMAGARD LIQUID vial is for single use only. Any vial that has been entered should be used promptly. Partially used vials should be discarded. GAMMAGARD LIQUID contains no preservative.
- Allow refrigerated product to come to room temperature before use. DO NOT MICROWAVE.
- Do not shake.
- Do not mix with other products.
- Do not use normal saline as a diluent. If dilution is desired, 5% dextrose in water (D5W) should be used as a diluent.
- The infusion line may be flushed with normal saline. An in-line filter is optional.
- Record the name and lot number of the product in the recipient's records.

2.5 Administration

Intravenous administration

Table 6: Infusion Rates for Intravenous Administration
 | PI | MMN | CIDP
Initial | 0.5 mL/kg/hr (0.8 mg/kg/min) for 30 minutes | Increasing rates of infusion starting at 0.5 mL/kg/h (0.8 mg/kg/min) | 0.5 mL/kg/hr (0.8 mg/kg/min)
Subsequent | Increase every 30 minutes (if tolerated) up to 5 mL/kg/hr (8 mg/kg/min) | Increasing to a maximum rate of 5.4 mL/kg/hr if tolerated (9 mg/kg/min) | Increase to a maximum rate of 5.4 mL/kg/hr if tolerated (9 mg/kg/min)

Monitor patient vital signs throughout the infusion. Certain adverse reactions (ARs) such as headaches, flushing, and changes in pulse rate and blood pressure may be related to the rate of infusion. Slow or stop infusion if adverse reactions occur. If symptoms subside promptly, the infusion may be resumed at a lower rate that does not result in recurrence of the symptoms.

Adverse reactions may occur more frequently in patients receiving immune globulin for the first time, upon switching brands or if there has been a long interval since the previous infusion.^2 In such cases, start at lower infusion rates and gradually increase as tolerated.

Ensure that patients with pre-existing renal insufficiency are not volume depleted. For patients over 65 years of age or judged to be at risk for renal dysfunction or thrombotic events, administer GAMMAGARD LIQUID at the minimum infusion rate practicable. In such cases, the maximal rate should be less than 3.3 mg/kg/min (<2 mL/kg/hr); consider discontinuation of administration if renal function deteriorates [see Warnings and Precautions (5.2, 5.4) and Use In Specific Populations (8.5)].

Subcutaneous administration for PI

Table 7: Infusion Rates for Subcutaneous Administration
 | 40 kg BW and greater | Under 40 kg BW
Initial | 30 mL/site at a rate of 20 mL/hr/site | 20 mL/site at a rate of 15 mL/hr/site
Maintenance | 30 mL/site at a rate of 20 to 30 mL/hr/site | 20 mL/site at a rate of 15 to 20 mL/hr/site

Selection of Infusion Site: Suggested areas for subcutaneous infusion of GAMMAGARD LIQUID are abdomen, thighs, upper arms, or lower back. Infusion sites should be at least two inches apart, avoiding bony prominences. Rotate sites each week.

Volume per Site: The weekly dose (mL) should be divided by 30 or 20, based on patient weight above, to determine the number of sites required. Simultaneous subcutaneous infusion at multiple sites can be facilitated by use of a multi-needle administration set.

Rate of Infusion for Patients 40 kg and greater (88 lbs): If multiple sites are used, the rate set on the pump should be the rate per site multiplied by the number of sites (e.g., 30 mL x 4 sites = 120 mL/hr). The number of simultaneous sites should be limited to 8, or maximum infusion rate of 240 mL/hr.

Rate of Infusion for Patients under 40 kg (88 lbs): If multiple sites are used, the rate set on the pump should be the rate per site multiplied by the number of sites (e.g., 20 mL x 3 sites = 60 mL/hr). The number of simultaneous sites should be limited to 8, or maximum infusion rate of 160 mL/hr.

Instructions for Subcutaneous Administration: Instruct patients to observe the following procedures:

1. Aseptic technique - Use aseptic technique when preparing and infusing GAMMAGARD LIQUID.
2. Assemble supplies - Set up a clean work area and gather all supplies necessary for the subcutaneous infusion: vial(s) of GAMMAGARD LIQUID, ancillary supplies, sharps container and pump. If GAMMAGARD LIQUID has already been pooled into a bag or a syringe, skip to Step 5.
3. Product preparation - Remove the protective cap from the vial to expose the center of the vial. Wipe the stopper with an alcohol pad and allow to dry.

4. Withdraw GAMMAGARD LIQUID from the vials - Attach a sterile syringe to a needle and draw air into the syringe barrel equal to the amount of product to be withdrawn. Inject the air into the vial and withdraw the desired volume of GAMMAGARD LIQUID. If multiple vials are required to achieve the desired dose, repeat this step.

5. Prepare the infusion pump and tubing - Follow the manufacturer's instructions for preparing the pump and administration tubing, if needed. Be sure to prime the pump tubing to ensure that no air is left in the tubing and needle.
6. Select the infusion sites - Select the number of infusion sites depending on the volume of the total dose. [See Dosage and Administration (2.5)] for recommended maximum volumes and rates. Potential sites for infusion include the back of arms, abdomen, thighs, and lower back (see Figure below). Ensure sites are at least 2 inches apart; avoid bony prominences.

7. Cleanse the infusion site(s) - Cleanse the infusion site(s) with an antiseptic skin preparation (e.g., alcohol pad) using a circular motion working from the center of the site and moving to the outside. Allow to dry.

8. Insert the needle - Choose the correct needle length to assure that GAMMAGARD LIQUID is delivered into the subcutaneous space. Grasp the skin and pinch at least one inch of skin between two fingers. Insert needle at a 90-degree angle with a darting motion into the subcutaneous tissue. Secure the needle.

9. Check for proper needle placement - Prior to the start of infusion, check each needle for correct placement to make sure that a blood vessel has not been punctured. Gently pull back on the attached syringe plunger and monitor for any blood return in the needle set. If you see any blood, remove and discard the needle set. Repeat priming and needle insertion steps in a different infusion site with a new needle set.

10. Secure the needle to the skin - Secure the needle(s) in place by applying a sterile protective dressing over the site.

11. Start infusion of GAMMAGARD LIQUID - Follow the manufacturer's instructions to turn pump on.
12. Document the infusion - Remove the peel-off label with product lot number and expiration date from the GAMMAGARD LIQUID vial and place in treatment diary/logbook to keep track of the product lots used. Keep the treatment diary/logbook current by recording the time, date, dose, product label and any reactions after each infusion.
13. Remove needle set - After the infusion is complete, remove the needle set and gently press a small piece of gauze over the needle insertion site and cover with a protective dressing. Discard any unused solution and disposable supplies in accordance with local requirements.

3 DOSAGE FORMS AND STRENGTHS

GAMMAGARD LIQUID is an aqueous solution containing 10% IgG (100 mg/mL).

4 CONTRAINDICATIONS

4.1 Hypersensitivity Reaction to Immune Globulins

GAMMAGARD LIQUID is contraindicated in patients who have a history of anaphylactic or severe systemic hypersensitivity reactions to administration of human immune globulin.

4.2 IgA Sensitive Patients with History of Hypersensitivity Reactions

GAMMAGARD LIQUID is contraindicated in IgA-deficient patients with antibodies to IgA and a history of hypersensitivity. Anaphylaxis has been reported with intravenous use of GAMMAGARD LIQUID and is theoretically possible following subcutaneous administration [see Warnings and Precautions (5.1)].

5 WARNINGS AND PRECAUTIONS

5.1 Hypersensitivity

Severe hypersensitivity reactions may occur, even in patients who had tolerated previous treatment with human normal immune globulin. In case of hypersensitivity, discontinue GAMMAGARD LIQUID infusion immediately and institute appropriate treatment.

GAMMAGARD LIQUID contains trace amount of IgA (average concentration of 37 μg/mL). Patients with antibodies to IgA have a greater risk of developing potentially severe hypersensitivity and anaphylactic reactions. GAMMAGARD LIQUID is contraindicated in patients with antibodies against IgA and a history of hypersensitivity reaction [see Contraindications (4.1)].

5.2 Renal Dysfunction/Failure

Acute renal dysfunction/failure, acute tubular necrosis, proximal tubular nephropathy, osmotic nephrosis, and death may occur upon use of IGIV treatment, especially those containing sucrose^3. Acute renal dysfunction/failure has been reported in association with infusions of GAMMAGARD LIQUID. Assure that patients are not volume depleted prior to the initiation of infusion of GAMMAGARD LIQUID. In patients who are at risk of developing renal dysfunction because of pre-existing renal insufficiency or predisposition to acute renal failure (such as diabetes mellitus, age greater than 65, volume depletion, sepsis, paraproteinemia, or patients receiving known nephrotoxic drugs, etc.), administer GAMMAGARD LIQUID intravenously at the minimum rate of infusion practicable (not exceeding 3.3 mg IgG/kg/min (<2 mL/kg/hr) [see Dosage and Administration (2.5)].

Periodic monitoring of renal function and urine output is particularly important in patients judged to be at increased risk for developing acute renal failure. Assess renal function, including measurement of blood urea nitrogen (BUN) and serum creatinine, before the initial infusion of GAMMAGARD LIQUID and again at appropriate intervals thereafter. If renal function deteriorates, consider discontinuation of GAMMAGARD LIQUID [see Dosage and Administration (2.5)].

5.3 Hyperproteinemia, Increased Serum Viscosity, and Hyponatremia

Hyperproteinemia, increased serum viscosity and hyponatremia may occur in patients receiving GAMMAGARD LIQUID. It is critical to distinguish true hyponatremia from pseudohyponatremia that is temporally or causally related to hyperproteinemia with concomitant decreased calculated serum osmolality or elevated osmolar gap. Treatment aimed at decreasing serum free water in patients with pseudohyponatremia may lead to volume depletion, a further increase in serum viscosity, and a predisposition to thromboembolic events.^4

5.4 Thrombosis

Thrombosis may occur following treatment with immune globulin products, including GAMMAGARD LIQUID. Risk factors may include advanced age, prolonged immobilization, hypercoagulable conditions, history of venous or arterial thrombosis, use of estrogens, indwelling central vascular catheters, hyperviscosity, and cardiovascular risk factors. Thrombosis may occur in the absence of known risk factors.

Consider baseline assessment of blood viscosity in patients at risk for hyperviscosity, including those with cryoglobulins, fasting chylomicronemia/markedly high triacylglycerols (triglycerides), or monoclonal gammopathies. For patients at risk of thrombosis, administer GAMMAGARD LIQUID at the minimum dose and infusion rate practicable. Ensure adequate hydration in patients before administration. Monitor for signs and symptoms of thrombosis and assess blood viscosity in patients at risk for hyperviscosity [see Boxed Warning, Dosage and Administration (2.5), Patient Counseling Information (17)].

5.5 Aseptic Meningitis Syndrome (AMS)

AMS may occur with immune globulin treatment, including GAMMAGARD LIQUID, administered intravenously or subcutaneously. AMS may occur more frequently in female patients. Discontinuation of immune globulin treatment has resulted in remission of AMS within several days without sequelae. The syndrome usually begins within several hours to two days following immune globulin treatment.

AMS is characterized by the following signs and symptoms: severe headache, nuchal rigidity, drowsiness, fever, photophobia, painful eye movements, nausea and vomiting [see Patient Counseling Information (17)]. Cerebrospinal fluid (CSF) studies frequently reveal pleocytosis up to several thousand cells per mm^3, predominantly from the granulocytic series, and elevated protein levels up to several hundred milligram/dL, but negative culture results. Conduct a thorough neurological examination on patients exhibiting such symptoms and signs, including CSF studies, to rule out other causes of meningitis.

5.6 Hemolysis

GAMMAGARD LIQUID, contains blood group antibodies that may act as hemolysins and induce in vivo coating of red blood cells (RBC) with immune globulin. This may cause a positive direct antiglobulin test [DAT (Coomb's test)].^5,6 Delayed hemolytic anemia can develop subsequent to GAMMAGARD LIQUID therapy due to enhanced RBC sequestration; acute hemolysis, consistent with intravascular hemolysis, has been reported [see Adverse Reactions (6)].^5-8

The following risk factors may be related to the development of hemolysis: high doses (e.g., ≥2 grams/kg, single administration or divided over several days) and non-O blood group.^5 Underlying inflammatory state in an individual patient may increase the risk of hemolysis,^5 but its role is uncertain.^8,9

Monitor patients for clinical signs and symptoms of hemolysis particularly patients with risk factors noted above. Consider appropriate laboratory testing in higher risk patients, including measurement of hemoglobin or hematocrit prior to infusion and within approximately 36 to 96 hours post infusion. If clinical signs and symptoms of hemolysis or a significant drop in hemoglobin or hematocrit have been observed, perform additional confirmatory laboratory testing. If transfusion is indicated for patients who develop hemolysis with clinically compromising anemia after receiving IGIV, perform adequate cross-matching to avoid exacerbating on-going hemolysis [see Warnings and Precautions (5.9)].

5.7 Transfusion-Related Acute Lung Injury (TRALI)

Non-cardiogenic pulmonary edema (TRALI) has been reported in patients following treatment with IGIV products, including GAMMAGARD LIQUID. TRALI is characterized by severe respiratory distress, pulmonary edema, hypoxemia, normal left ventricular function, and fever. Symptoms typically occur within 1 to 6 hours after treatment.

Monitor patients for pulmonary adverse reactions [see Patient Counseling Information (17)]. If TRALI is suspected, perform appropriate tests for the presence of anti-neutrophil and anti-HLA antibodies in both the product and patient serum. TRALI may be managed using oxygen therapy with adequate ventilatory support.

5.8 Transmissible Infectious Agents

Because GAMMAGARD LIQUID is made from human blood, it may carry a risk of transmitting infectious agents, e.g., viruses, the variant Creutzfeldt-Jakob disease (vCJD) agent, and theoretically, the Creutzfeldt-Jakob disease agent. This also applies to unknown or emerging viruses and other pathogens. No confirmed cases of viral transmission or vCJD have been associated with GAMMAGARD LIQUID.

All infections thought by a physician to possibly have been transmitted by this product should be reported by the physician or other healthcare provider to Takeda Pharmaceuticals U.S.A., Inc. at 1-877-TAKEDA-7 (1-877-825-3327) (in the U.S.).

5.9 Monitoring: Laboratory Tests

- Periodic monitoring of renal function and urine output is particularly important in patients judged to be at increased risk of developing acute renal failure. Assess renal function, including measurement of blood urea nitrogen (BUN) and serum creatinine, before the initial infusion of GAMMAGARD LIQUID and at appropriate intervals thereafter.
- Consider baseline assessment of blood viscosity in patients at risk for hyperviscosity, including those with cryoglobulins, fasting chylomicronemia/markedly high triacylglycerols (triglycerides), or monoclonal gammopathies, because of the potentially increased risk of thrombosis.^3,4
- If signs and/or symptoms of hemolysis are present after an infusion of GAMMAGARD LIQUID, perform appropriate laboratory testing for confirmation.
- If TRALI is suspected, perform appropriate tests for the presence of anti-neutrophil antibodies and anti-HLA antibodies in both the product and the patient's serum.

5.10 Interference with Laboratory Tests

After infusion of IgG, the transitory rise of the various passively transferred antibodies in the patient's blood may yield false positive serological testing results, with the potential for misleading interpretation. Passive transmission of antibodies to erythrocyte antigens (e.g., A, B, and D) may cause a positive direct or indirect antiglobulin (Coombs') test.

Administration of immune globulin products, including GAMMAGARD LIQUID, can lead to false positive readings in assays that depend on detection of beta-D-glucans for diagnosis of fungal infections; this may persist during the weeks following infusion of the product.

6 ADVERSE REACTIONS

Primary Immunodeficiency (PI)

Intravenous administration:

The serious adverse reaction (AR) seen during intravenous treatment in the clinical studies for PI was aseptic meningitis. The most common adverse reactions for PI (observed in ≥5% of subjects) were headache, fatigue, pyrexia, nausea, chills, rigors, pain in extremity, diarrhea, migraine, dizziness, vomiting, cough, urticaria, asthma, pharyngolaryngeal pain, rash, arthralgia, myalgia, oedema peripheral, pruritus, and cardiac murmur.

Subcutaneous Administration:

No serious adverse reactions were observed during the clinical study of subcutaneous treatment. The most common adverse reactions during subcutaneous treatment (observed in ≥5% of PI subjects) were infusion site (local) event, headache, fatigue, heart rate increased, pyrexia, abdominal pain upper, nausea, vomiting, asthma, blood pressure systolic increased, diarrhea, ear pain, aphthous stomatitis, migraine, oropharyngeal pain, and pain in extremity.

Multifocal Motor Neuropathy (MMN)

The serious adverse reactions in the clinical study for MMN were pulmonary embolism and blurred vision. The most common adverse reactions for MMN (observed in ≥5% of subjects) were headache, chest discomfort, muscle spasms, muscular weakness, nausea, oropharyngeal pain, and pain in extremity.

Chronic Inflammatory Demyelinating Polyneuropathy (CIDP)

The most common adverse reactions observed in ≥5% of clinical study subjects receiving GAMMAGARD LIQUID for CIDP were headache, pyrexia, anemia, leukopenia, neutropenia, illness, blood creatinine increased, dizziness, migraine, somnolence, tremor, nasal dryness, abdominal pain upper, vomiting, chills, nasopharyngitis, and pain in extremity.

6.1 Clinical Trials Experience

Because clinical studies are conducted under widely varying conditions, adverse reaction rates observed in the clinical studies of a drug cannot be directly compared to rates in the clinical studies of another drug and may not reflect the rates observed in clinical practice.

Treatment of Primary Immunodeficiency (Intravenous)

The safety of GAMMAGARD LIQUID intravenous infusion was evaluated in 61 subjects.

Fifteen adverse reactions in 8 subjects were serious. Of these, two episodes of aseptic meningitis in one subject were deemed possibly related to infusion of GAMMAGARD LIQUID.

There were 400 non-serious adverse reactions. Of these, 217 were rated as mild (transient discomfort that resolves spontaneously or with minimal intervention), 164 were rated as moderate (limited impairment of function and resolves spontaneously or with minimal intervention with no sequelae), and 19 were rated as severe (marked impairment of function or can lead to temporary inability to resume normal life pattern; requires prolonged intervention or results in sequelae). All of the severe non-serious adverse experiences were transient, did not lead to hospitalization, and resolved without complication. One subject withdrew from the study due to a non-serious adverse experience (papular rash).

Adverse reactions with a frequency of ≥5% (defined as adverse events occurring during or within 72 hours of infusion or any causally related event occurring within the study period) are shown in Table 8.

Table 8: Adverse Reactions Occurring in ≥5% of Subjects with PI (Intravenous Administration)
Events | By Infusion N (%); (N=1812 Infusions) | By Subject N (%); (N=61 Subjects)
Headache | 94 (5.2%) | 29 (47.5%)
Fatigue | 33 (1.8%) | 14 (23.0%)
Pyrexia | 28 (1.5%) | 17 (27.9%)
Nausea | 17 (0.9%) | 11 (18.0%)
Chills | 14 (0.8%) | 8 (13.1%)
Rigors | 14 (0.8%) | 8 (13.1%)
Pain in extremity | 13 (0.7%) | 7 (11.5%)
Diarrhea | 12 (0.7%) | 9 (14.8%)
Migraine | 12 (0.7%) | 4 (6.6%)
Dizziness | 11 (0.6%) | 8 (13.1%)
Vomiting | 11 (0.6%) | 9 (14.8%)
Cough | 9 (0.5%) | 8 (13.1%)
Urticaria | 9 (0.5%) | 5 (8.2%)
Asthma | 7 (0.4%) | 6 (9.8%)
Pharyngolaryngeal pain | 7 (0.4%) | 5 (8.2%)
Rash | 6 (0.3%) | 4 (6.6%)
Arthralgia | 5 (0.3%) | 4 (6.6%)
Myalgia | 5 (0.3%) | 5 (8.2%)
Oedema peripheral | 5 (0.3%) | 5 (8.2%)
Pruritus | 5 (0.3%) | 4 (6.6%)
Cardiac murmur | 4 (0.2%) | 4 (6.6%)

Pooled analysis of 4 short term clinical studies with 106 subjects (total of 854 infusions) showed no differences in the safety profile of GAMMAGARD LIQUID. These short-term studies were designed to stabilize the immune globulin treatment or as a safety follow-up study. They were not designed to study the safety, efficacy and tolerability of GAMMAGARD LIQUID. No additional adverse reactions were reported during the study periods.

Treatment of Primary Immunodeficiency (Subcutaneous)

The safety of GAMMAGARD LIQUID in subcutaneous infusion was evaluated in 47 subjects.

Adverse reactions with a frequency of ≥5% (defined as adverse events occurring during or within 72 hours of infusion or any causally related event occurring within the study period) are shown in Table 9.

Table 9: Adverse Reactions Occurring in ≥5% of Subjects with PI (Subcutaneous Administration)
Events | By Infusion N (%); (N=2294 infusions) | By Subject N (%); (N=47 Subjects)
Infusion site (local) event | 55 (2.4%) | 21 (44.7%)
Headache | 31 (1.4%) | 19 (40.4%)
Fatigue | 11 (0.5%) | 7 (14.9%)
Heart rate increased | 11 (0.5%) | 3 (6.4%)
Pyrexia | 11 (0.5%) | 9 (19.1%)
Abdominal pain upper | 9 (0.4%) | 5 (10.6%)
Nausea | 7 (0.3%) | 3 (6.4%)
Vomiting | 7 (0.3%) | 5 (10.6%)
Asthma | 6 (0.3%) | 4 (8.5%)
Blood pressure systolic increased | 6 (0.3%) | 3 (6.4%)
Diarrhea | 5 (0.2%) | 3 (6.4%)
Ear pain | 4 (0.2%) | 3 (6.4%)
Aphthous stomatitis | 3 (0.1%) | 3 (6.4%)
Migraine | 3 (0.1%) | 3 (6.4%)
Oropharyngeal pain | 3 (0.1%) | 3 (6.4%)
Pain in extremity | 3 (0.1%) | 3 (6.4%)

Of the 348 non-serious adverse reactions, 228 were rated as mild (transient discomfort that resolves spontaneously or with minimal intervention), 112 were rated as moderate (limited impairment of function and resolves spontaneously or with minimal intervention with no sequelae), and 8 were rated as severe (marked impairment of function or can lead to temporary inability to resume normal life pattern; requires prolonged intervention or results in sequelae). Neither of the severe adverse reactions required hospitalization or resulted in sequelae.

Local Adverse Reactions:

Local adverse reactions reported as mild (transient discomfort that resolves spontaneously or with minimal intervention) were rash, erythema, edema, hemorrhage, and irritation. Local adverse reactions reported as mild or moderate (limited impairment of function and resolves spontaneously or with minimal intervention with no sequelae) were pain, hematoma, pruritus, and swelling.

One subject withdrew from the study after 10 treatments with GAMMAGARD LIQUID subcutaneous infusion (2.5 months) due to increased fatigue and malaise.

The overall rate of local adverse reactions (excluding infections) during subcutaneous treatment was 2.4% per infusion. In subcutaneous naïve subjects, the incidence of local adverse reactions (N=1757 infusions) was 2.8% (2.2% mild and 0.6% moderate with no severe adverse reactions). In the subjects who were subcutaneous experienced (N=537 infusions), the incidence of local adverse reactions was 1.1% (1.1% mild, and no moderate or severe adverse reactions).

After all subcutaneous doses were adjusted, only one subject did not reach the maximum rate allowed in the protocol for one or more infusions, 20 mL/site/hour if weight was below 40 kg and 30/mL/hour for weight 40 kg and greater. Overall, 70% (31 of 44) of subjects opted for the highest rate for all infusions. No subject limited the infusion rate due to an adverse reaction. Median duration of each weekly infusion was 1.2 hours (range: 0.8-2.3 hours). The rate set on the pump was the rate per site multiplied by the number of sites, with no maximum.

During subcutaneous treatment, 99.8% of infusions were completed without a reduction, interruption, or discontinuation for tolerability reasons. The proportion of subjects who experienced local adverse reactions (excluding infections) was highest immediately following the switch from intravenous to subcutaneous treatment in all age groups. The rate of local adverse reactions per infusion immediately after switching from intravenous to subcutaneous treatment was 4.9% (29/595), decreasing to 1.5% (8/538) by the end of the study and to 1.1% (10/893) in the Study Extension. There was a decrease of local adverse reactions over subsequent subcutaneous infusions.

Eight (17%) subjects experienced a local adverse reaction during the first infusion, but that decreased to 1 (2.2%) for subsequent infusions, ranging from 0 to 4 (8.7%) during the first year of subcutaneous treatment. No subject reported a local adverse reaction from week 53 to end of study at week 68.

Analysis of a short-term follow-up safety study of 10 subjects who were treated with subcutaneous administration of GAMMAGARD LIQUID (total of 218 infusions) showed no differences in the safety profile. The follow-up safety study was not designed to study the safety, efficacy and tolerability of GAMMAGARD LIQUID and no additional adverse reactions were reported during the study period.

Treatment of Multifocal Motor Neuropathy (Intravenous)

The safety of GAMMAGARD LIQUID was evaluated in 44 subjects with MMN who received a total of 983 infusions. Two serious adverse reactions, pulmonary embolism and blurred vision, occurred.

In the study, among the 317 non-serious adverse reactions, 176 were considered ARs. Of these, 126 were mild (transient discomfort that resolves spontaneously or with minimal intervention), 37 were moderate (limited impairment of function and resolves spontaneously or with minimal intervention with no sequelae) and 13 were severe (marked impairment of function or can lead to temporary inability to resume normal life pattern; requires prolonged intervention or results in sequelae).

Adverse reactions with a frequency ≥5% (defined as adverse events occurring during or within 72 hours of infusion or any causally related event occurring within the study period) are shown in Table 10.

Table 10: Adverse Reactions Occurring in ≥5% of MMN Subjects
Events | GAMMAGARD LIQUID |  | Placebo
Events | By Infusion; N (%); (N=983 Infusions) | By Subject; N (%); (N=44 Subjects) | By Infusion; N (%); (N=129 Infusions) | By Subject; N (%); (N=43 Subjects)
Headache | 28 (2.85%) | 14 (31.82%) | 3 (2.33%) | 2 (4.65%)
Chest Discomfort | 3 (0.31%) | 3 (6.82%) | 0 (0.00%) | 0 (0.00%)
Muscle Spasms | 3 (0.31%) | 3 (6.82%) | 0 (0.00%) | 0 (0.00%)
Muscular weakness | 4 (0.41%) | 3 (6.82%) | 1 (0.78%) | 1 (2.33%)
Nausea | 28 (2.85%) | 3 (6.82%) | 2 (1.55%) | 1 (2.33%)
Oropharyngeal pain | 4 (0.41%) | 3 (6.82%) | 0 (0.00%) | 0 (0.00%)
Pain in extremity | 4 (0.41%) | 3 (6.82%) | 1 (0.78%) | 1 (2.33%)

Treatment of Chronic Inflammatory Demyelinating Polyneuropathy (Intravenous)

The safety of GAMMAGARD LIQUID was evaluated in a clinical study of 20 adult subjects with CIDP. A total of 389 infusions of GAMMAGARD LIQUID were administered during the study.

Fourteen out of the 20 subjects reported 60 adverse events; 9 experienced mild events (transient discomfort that resolves spontaneously or with minimal intervention), 3 had moderate events (limited impairment of function and resolves spontaneously or with minimal intervention with no sequelae), and 2 experienced severe events (marked impairment of function or can lead to a temporary inability to resume normal life pattern; requires prolonged intervention or results in sequelae). There were 39 ARs in 13 subjects (65%), and 31 related to GAMMAGARD LIQUID in 11 subjects (55%). One subject (5%) experienced one severe AR (headache) related to GAMMAGARD LIQUID. No AR resulted in early discontinuation or death, and no serious AR was reported.

Adverse reactions with a frequency ≥5% (defined as adverse events occurring during or within 72 hours of infusion or any causally related event occurring within the study period) are shown in Table 11.

Table 11: Adverse Reactions Occurring in ≥5% of CIDP Subjects
Events | By Infusion N (%) (N=389 Infusions) | By Subject N (%) (N=20 Subjects)
Headache | 20 (5.1%) | 8 (40.0%)
Pyrexia | 3 (0.8%) | 2 (10.0%)
Abdominal pain upper | 1 (0.3%) | 1 (5.0%)
Anemia | 1 (0.3%) | 1 (5.0%)
Blood creatinine increased | 1 (0.3%) | 1 (5.0%)
Chills | 2 (0.5%) | 1 (5.0%)
Dizziness | 1 (0.3%) | 1 (5.0%)
Illness | 1 (0.3%) | 1 (5.0%)
Leukopenia | 1 (0.3%) | 1 (5.0%)
Migraine | 1 (0.3%) | 1 (5.0%)
Nasal Dryness | 1 (0.3%) | 1 (5.0%)
Nasopharyngitis | 1 (0.3%) | 1 (5.0%)
Neutropenia | 1 (0.3%) | 1 (5.0%)
Pain in extremity | 1 (0.3%) | 1 (5.0%)
Somnolence | 1 (0.3%) | 1 (5.0%)
Tremor | 1 (0.3%) | 1 (5.0%)
Vomiting | 1 (0.3%) | 1 (5.0%)

6.2 Postmarketing Experience

Because postmarketing reporting of adverse reactions is voluntary and from a population of uncertain size, it is not always possible to reliably estimate the frequency of these reactions or establish a causal relationship to product exposure.

Intravenous Adverse Reactions

Blood and Lymphatic System Disorders: Hemolysis
Immune System Disorders: Anaphylactic shock
Nervous System Disorders: Cerebral vascular accident, transient ischemic attack, tremor
Cardiac Disorders: Myocardial infarction
Vascular Disorders: Deep vein thrombosis, hypotension
Respiratory, Thoracic and Mediastinal Disorders: Pulmonary embolism, pulmonary edema
Skin and Subcutaneous Tissue Disorders: Hyperhidrosis
General Disorders and Administration-Site Conditions: Chest pain
Investigations: Coombs direct test positive, oxygen saturation decreased
Injury, Poisoning and Procedural Complications: Transfusion-related acute lung injury

Subcutaneous Adverse Reactions

Immune System Disorders: Hypersensitive
Musculoskeletal and Connective Tissue Disorders: Myalgia
General Disorders and Administration-Site Conditions: Chills

In addition to the adverse reactions listed above, the following reactions have been identified for immune globulin products administered intravenously:

Renal and Urinary Disorders: Osmotic nephropathy
Respiratory, Thoracic and Mediastinal Disorders: Cyanosis, hypoxemia, bronchospasm, apnea, Acute Respiratory Distress Syndrome (ARDS)
Integumentary: Bullous dermatitis, epidermolysis, erythema multiforme, Stevens-Johnson Syndrome
Vascular Disorders: Cardiac arrest, vascular collapse
Nervous System Disorders: Coma, seizures, loss of consciousness
Blood and Lymphatic System Disorders: Pancytopenia
Gastrointestinal: Hepatic dysfunction

The adverse reactions listed below have been identified and reported with the use of another immune globulin products administered subcutaneously:

Immune System Disorders: Anaphylactic reaction
Nervous System Disorders: Paresthesia, tremor
Cardiac Disorders: Tachycardia
Vascular Disorders: Hypotension
Respiratory, Thoracic and Mediastinal Disorders: Dyspnea, laryngospasm
General Disorders and Administration-Site Conditions: Chest discomfort, injection site reaction (including induration, warmth)

7 DRUG INTERACTIONS

Passive transfer of antibodies may transiently impair the immune response to live attenuated virus vaccines such as mumps, rubella and varicella for up to 6 months, and for a year or more to measles (rubeola). Inform the immunizing physician of recent therapy with GAMMAGARD LIQUID so that appropriate precautions can be taken [see Patient Counseling Information (17)].

8 USE IN SPECIFIC POPULATIONS

8.1 Pregnancy

Risk Summary

Animal reproduction studies have not been conducted with GAMMAGARD LIQUID. It is not known whether GAMMAGARD LIQUID can cause fetal harm when administered to a pregnant woman or can affect reproduction capacity. Immune globulins cross the placenta from maternal circulation increasingly after 30 weeks of gestation. GAMMAGARD LIQUID should be given to a pregnant woman only if clearly indicated.

The background risk of major birth defects and miscarriage for the indicated population is unknown. In the U.S. general population, the estimated background risk of major birth defects and miscarriage in clinically recognized pregnancies is 2-4% and 15-20%, respectively.

8.2 Lactation

Risk Summary

There is no information regarding the presence of GAMMAGARD LIQUID in human milk, its effects on the breastfed infant or its effects on milk production. The developmental and health benefits of breastfeeding should be considered along with the mother's clinical need for GAMMAGARD LIQUID and any potential adverse effects on the breastfed infant from GAMMAGARD LIQUID or from the underlying maternal condition.

8.4 Pediatric Use

Treatment of Primary Immunodeficiency (PI)

GAMMAGARD LIQUID administered intravenously was evaluated in 15 pediatric subjects with PI (7 subjects aged 2 to <12 years and 8 subjects aged 12 to <16 years) in a multicenter clinical study. GAMMAGARD LIQUID administered subcutaneously was evaluated in 18 pediatric subjects with PI (14 subjects aged 2 to <12 years and 4 subject aged 12 to <16 years) in another multicenter clinical study. The safety and efficacy profiles were similar to adult subjects. No pediatric-specific dose requirements were necessary to achieve the desired serum IgG levels.

Safety and efficacy of GAMMAGARD LIQUID in pediatric patients below the age of 2 have not been established.

Treatment of Multifocal Motor Neuropathy (MMN) and Chronic Inflammatory Demyelinating Polyneuropathy (CIDP)

Safety and effectiveness in pediatric patients with MMN and CIDP have not been established.

8.5 Geriatric Use

Treatment of Primary Immunodeficiency (PI)

Limited information is available for the geriatric use of GAMMAGARD LIQUID. GAMMAGARD LIQUID administered intravenously and subcutaneously was evaluated in two PI studies with a total of 8 subjects over the age of 65 years. No differences in safety or efficacy were observed for this group. Monitor patients who are at an increased risk for developing renal failure or thrombotic events. Do not exceed the recommended dose. Infuse at the minimum intravenous infusion rate practicable [see Boxed Warning, Warnings and Precautions (5.2, 5.4) and Dosage and Administration (2.5)].

Treatment of Multifocal Motor Neuropathy (MMN)

GAMMAGARD LIQUID was administered intravenously for treatment of MMN in 5 subjects aged 65 years and above. There was an insufficient number of subjects aged 65 years and above to determine whether they respond differently from younger subjects [see Boxed Warning, Warnings and Precautions (5.2, 5.4) and Dosage and Administration (2.5)].

Treatment of Chronic Inflammatory Demyelinating Polyneuropathy (CIDP)

GAMMAGARD LIQUID was administered intravenously for the treatment of CIDP in 5 subjects aged 65 years and above and 15 subjects aged below 65 years. There was an insufficient number of subjects aged 65 years and above to determine whether they respond differently from younger subjects. [see Boxed Warning, Warnings and Precautions (5.2, 5.4) and Dosage and Administration (2.5)].

10 OVERDOSAGE

With intravenous administration, overdose of GAMMAGARD LIQUID may lead to fluid overload and hyperviscosity. Patients at risk of complications of fluid overload and hyperviscosity include elderly patients and those with cardiac or renal impairment.

11 DESCRIPTION

GAMMAGARD LIQUID is a ready-for-use sterile, liquid preparation of highly purified and concentrated immunoglobulin G (IgG) antibodies. The distribution of the IgG subclasses is similar to that of normal plasma. The Fc and Fab functions are maintained in GAMMAGARD LIQUID. Pre-kallikrein activator activity is not detectable. GAMMAGARD LIQUID contains 100 mg/mL protein. At least 98% of the protein is immune globulin, the average immunoglobulin A (IgA) concentration is 37 µg/mL, and immunoglobulin M is present in trace amounts. GAMMAGARD LIQUID contains a broad spectrum of IgG antibodies against bacterial and viral agents. Glycine (0.25M) serves as a stabilizing and buffering agent. There are no added sugars, sodium or preservatives. The pH is 4.6 to 5.1. The osmolality is 240 to 300 mOsmol/kg, which is similar to physiological osmolality (285 to 295 mOsmol/kg).

GAMMAGARD LIQUID is manufactured from large pools of human plasma. IgG preparations are purified from plasma pools using a modified Cohn-Oncley cold ethanol fractionation process, as well as cation and anion exchange chromatography.

Screening against potentially infectious agents begins with the donor selection process and continues throughout plasma collection and plasma preparation. Each individual plasma donation used in the manufacture of GAMMAGARD LIQUID is collected only at FDA approved blood establishments and is tested by FDA licensed serological tests for Hepatitis B Surface Antigen (HBsAg), and for antibodies to Human Immunodeficiency Virus (HIV-1/HIV-2) and Hepatitis C Virus (HCV) in accordance with U.S. regulatory requirements. As an additional safety measure, mini-pools of the plasma are tested for the presence of HIV-1 and HCV by FDA licensed Nucleic Acid Testing (NAT) and found to be negative.

To further improve the margin of safety, validated virus inactivation/removal steps have been integrated into the manufacturing and formulation processes, namely solvent/detergent (S/D) treatment,^10 35 nm nanofiltration, and a low pH incubation at elevated temperature (30 C to 32 C). The S/D process includes treatment with an organic mixture of tri-n-butyl phosphate, octoxynol 9 and polysorbate 80 at 18 C to 25 C for a minimum of 60 minutes. S/D treatment inactivates the lipid-enveloped viruses investigated to below detection limits within minutes.^12

In vitro virus spiking studies have been used to validate the capability of the manufacturing process to inactivate and remove viruses. To establish the minimum applicable virus clearance capacity of the manufacturing process, virus clearance studies were performed under extreme conditions (e.g., at minimum S/D concentrations, incubation time and temperature for the S/D treatment).

Virus clearance studies for GAMMAGARD LIQUID performed in accordance with good laboratory practices are summarized in Table 12.

Table 12: Three Dedicated Independent Virus Inactivation/Removal Steps Mean Log10 Reduction Factors [For the calculation of these RF data from virus clearance study reports, applicable manufacturing conditions were used. Log10 RFs on the order of 4 or more are considered effective for virus clearance in accordance with the Committee for Medicinal Products for Human Use (CHMP, formerly CPMP) guidelines.] (RFs) For Each Virus and Manufacturing Step
Virus type | Enveloped RNA |  |  | Enveloped DNA | Non-enveloped RNA |  | Non-enveloped DNA
Family | Retroviridae | Flaviviridae |  | Herpesviridae | Picornaviridae |  | Parvoviridae
Virus | HIV-1 | BVDV | WNV | PRV | HAV | EMCV | MMV
SD treatment | >4.5 | >6.2 | n.a. | >4.8 | n.d. | n.d. | n.d
35 nm nanofiltration | >4.5 | >5.1 | >6.2 | >5.6 | 5.7 | 1.4 | 2.0
Low pH treatment | >5.8 | >5.5 | >6.0 | >6.5 | n.d. [No RF obtained due to immediate neutralization of HAV by the anti-HAV antibodies present in the product.] | >6.3 | 3.1
Overall log reduction factor (ORF) | >14.8 | >16.8 | >12.2 | >16.9 | 5.7 | >7.7 | 5.1
Abbreviations: HIV-1, Human Immunodeficiency Virus Type 1; BVDV, Bovine Viral Diarrhea Virus (model for Hepatitis C Virus and other lipid enveloped RNA viruses); WNV, West Nile Virus; PRV, Pseudorabies Virus (model for lipid enveloped DNA viruses, including Hepatitis B Virus); EMCV, Encephalomyocarditis Virus (model for non-lipid enveloped RNA viruses, including Hepatitis A virus [HAV]); MMV, Mice Minute Virus (model for non-lipid enveloped DNA viruses, including B19 virus [B19V]); n.d. (not done), n.a. (not applicable).

12 CLINICAL PHARMACOLOGY

12.1 Mechanism of Action

GAMMAGARD LIQUID supplies a broad spectrum of opsonizing and neutralizing IgG antibodies against a wide variety of bacterial and viral agents. GAMMAGARD LIQUID also contains a spectrum of antibodies capable of interacting with and altering the activity of cells of the immune system as well as antibodies capable of reacting with cells such as erythrocytes. The role of these antibodies and the mechanism of action of IgG in GAMMAGARD LIQUID have not been fully elucidated.

The mechanism of action of immunoglobulins in the treatment of CIDP in adults has not been fully elucidated but may include immunomodulatory effects.

12.3 Pharmacokinetics

Treatment of Primary Immunodeficiency (Intravenous)

Following intravenous infusion, IGIV products show a biphasic decay curve. The initial (α) phase is characterized by an immediate post-infusion peak in serum IgG and is followed by rapid decay due to equilibration between the plasma and extravascular fluid compartments. The second (β) phase is characterized by a slower and constant rate of decay. The commonly cited "normal" half-life of 18 to 25 days is based on studies in which tiny quantities of radiolabeled IgG are injected into healthy individuals. When radiolabeled IgG was injected into patients with hypogammaglobulinemia or agammaglobulinemia, highly variable half-lives ranging from 12 to 40 days were observed. In other radiolabeled studies, high serum concentrations of IgG and hypermetabolism associated with fever and infection have been seen to coincide with a shortened IgG half-life.

In contrast, pharmacokinetic studies in immunodeficient patients are based on the decline of IgG concentrations following infusion of large quantities of immune globulin. In such studies, investigators have reported uniformly prolonged half-lives of 26 to 35 days. Pharmacokinetic parameters for GAMMAGARD LIQUID were determined from total IgG levels following the fourth infusion in subjects with primary humoral immunodeficiency (N=61) treated intravenously with the product every 3 or 4 weeks according to the regimen used prior to entering the study. Of these, 57 had sufficient pharmacokinetic data to be included in the dataset. The median weight-adjusted dose per subject was 455mg/kg/4 weeks with a range of 262 to 710. Pharmacokinetic parameters are presented in Table 13.

Table 13: Summary of Intravenous Pharmacokinetic Parameters in 57 Subjects
Parameter | Median | 95% Confidence Interval
Dose of IgG (milligram/kg/4 weeks) | 455 | Range: 262-710
Elimination Half-Life (T ½ days) | 35 | (31, 42)
AUC0-21d (milligram∙days/dL) | 29139 | (27494, 30490)
Cmax (Peak, milligram/dL) | 2050 | (1980, 2200)
Cmin (Trough, milligram/dL) | 1030 | (939, 1110)
Incremental recovery (milligram/dL)/(milligram/kg) | 2.3 | (2.2, 2.6)
Abbreviations: AUC=area under the curve,
Cmax=maximum concentration
Cmin=minimum concentration.

Median IgG trough levels were maintained between 960 to 1120mg/dL. These dosing regimens-maintained serum trough IgG levels generally considered adequate to prevent bacterial infections. The elimination half-life of GAMMAGARD LIQUID (35 days) was similar to that reported for other IGIV products.

Treatment of Primary Immunodeficiency (Subcutaneous)

Pharmacokinetic (PK) parameters of subcutaneously administered GAMMAGARD LIQUID were evaluated in subjects with primary immunodeficiency (PI) who were 12 years and older during a clinical study [see Clinical Studies (14)].

Subjects were treated intravenously for 12 weeks with GAMMAGARD LIQUID and then switched to weekly subcutaneous GAMMAGARD LIQUID infusions. Initially, all subjects were treated for a minimum of 12 weeks at a subcutaneous dose that was 130% of the intravenous dose. A comparison of the area under the curve (AUC) for intravenous and subcutaneous infusions done on the first 15 adult subjects determined that the subcutaneous dose required to provide an exposure from subcutaneous administration that was not inferior to the exposure from intravenous administration was 137% of the intravenous dose. Subsequently, all subjects were treated with this dose for 6 weeks after which the dose was individualized for all subjects using IgG trough levels, as described below. After a minimum of 8 weeks at this subcutaneous dose, a PK evaluation was conducted on subjects 12 years of age or older (N=32).

The mean adjusted dose at the end of the study was 137.3% (125.7 to 150.8) of the intravenous dose for subjects 12 years and older, and 141.0% (100.5 to 160.0) for subjects under the age of 12. Thus, a significant dosing difference was not required for children. At this dose adjustment, the geometric mean ratio of the AUC for subcutaneous vs. intravenous GAMMAGARD LIQUID administration was 95.2% (90% confidence limit: 92.3 to 98.2). The peak IgG level occurred 2.9 (1.2 to 3.2) days after subcutaneous administration.

Pharmacokinetic parameters of GAMMAGARD LIQUID administered intravenously versus subcutaneously in the clinical study are shown in Table 14. The mean peak IgG level was lower (1393 ± 289 mg/dL) during subcutaneous treatment than with intravenous treatment (2240 ± 536 mg/dL), consistent with lower weekly doses compared with doses administered every 3 or 4 weeks intravenously. In contrast, the mean trough level was higher when GAMMAGARD LIQUID was given subcutaneously (1202 ± 282 mg/dL) than when it was given intravenously (1050 ± 260 mg/dL), a result of both higher monthly dose and more frequent dosing. The median IgG trough level during intravenous treatment in this clinical study, 1010 mg/dL (95% CI: 940 to 1240), was similar to the median IgG trough level of 1030 mg/dL (95% CI: 939 to 1110) during intravenous treatment as shown in Table 13. By contrast, the median IgG trough level during subcutaneous treatment was higher, at 1260 mg/dL (95% CI: 1060 to 1400).

Table 14: Pharmacokinetic Parameters of Subcutaneously Administered GAMMAGARD LIQUID Compared With GAMMAGARD LIQUID Administered Intravenously
 |  | Subcutaneous Administration | Intravenous Administration
Number of Subjects |  | 32 | 32
Dose [Weekly equivalent dose] (milligram/kg)
 | Mean ± SD | 182.6 ± 48.4 | 133.2 ± 36.9
 | Range (min to max) | 94.2 to 293.8 | 62.7 to 195.4
IgG Peak Levels (milligram/dL)
 | Mean ± SD | 1393 ± 289 | 2240 ± 536
 | Range (min to max) | 734 to 1900 | 1130 to 3610
IgG Trough Levels (milligram/dL)
 | Mean ± SD | 1202 ± 282 | 1050 ± 260
 | Range (min to max) | 621 to 1700 | 532 to 1460
AUC [Standardized to a 7-day interval] (days*milligram/dL)
 | Mean ± SD | 9176 ± 1928 | 9958 ± 2274
 | Range (min to max) | 4695 to 12468 | 5097 to 13831
Clearance [mL/kg/day]
 | Mean ± SD | 2.023 ± 0.528 | 1.355 ± 0.316
 | Range (min to max) | 1.225 to 3.747 | 0.880 to 2.340

Treatment of Multifocal Motor Neuropathy (Intravenous)

No full pharmacokinetic study was conducted in subjects with MMN. However, trough levels of IgG were measured in this population (n = 44; five 12 week study parts). The median serum trough level of total IgG over all study parts regardless of dosing intervals and length of infusion cycles, was 1640 (95% confidence interval: 1570 to 1710) mg/dL. During placebo administration, the median trough level was 1235 (95% CI: 1060 to 1360) mg/dL. The relationship between serum IgG concentration and efficacy was not assessed.

Treatment of Chronic Inflammatory Demyelinating Polyneuropathy (Intravenous)

The full pharmacokinetic profile of GAMMAGARD LIQUID was not evaluated but serum trough IgG levels were measured in subjects with CIDP following administrations of GAMMAGARD LIQUID in the clinical study [see Clinical Studies (14)]. In 16 subjects who had previously received placebo in a preceding study and started administration of GAMMAGARD LIQUID after relapse, the median (range, number of subjects) serum trough IgG levels at baseline, Week 13, and Week 25 were 1220 (449 to 2220, N=16) mg/dL, 1810 (590 to 3200, N=13) mg/dL, and 1615 (712 to 3480, N=14) mg/dL, respectively.

13 NONCLINICAL TOXICOLOGY

13.1 Carcinogenesis, Mutagenesis, Impairment of Fertility

Long-term animal studies have not been conducted to evaluate the carcinogenic potential of GAMMAGARD LIQUID or its effect on fertility.

An in vitro mutagenicity test was performed with GAMMAGARD LIQUID. No evidence of mutagenicity was observed.

13.2 Animal Toxicology and/or Pharmacology

In single-dose toxicity studies GAMMAGARD LIQUID revealed no adverse effects at doses of 5000 mg/kg or 2000 mg/kg in mice and rats, respectively. Repeat-dose toxicity studies were not conducted.

14 CLINICAL STUDIES

Treatment of Primary Immunodeficiency (Intravenous)

Intravenous use of GAMMAGARD LIQUID is supported by a study in subjects (N=61) who were treated with 300 to 600 mg/kg every 21 to 28 days for 12 months. The age range of subjects was 6 to 72 years, with 54% female and 46% male, and 93% Caucasian, 5% African American, and 2% Asian. Three subjects were excluded from the per-protocol analysis due to non-study product related reasons. The annualized rate of prespecified acute serious bacterial infections, i.e., the mean number of prespecified acute serious bacterial infections per subject per year, was studied (see Table 15).

Table 15: Summary of Validated Acute Serious Bacterial Infections for the Per-Protocol Analysis
 | Number of Events
Validated Infections [Serious acute bacterial infections were defined by FDA and met specific diagnostic requirements]
Bacteremia / Sepsis | 0
Bacterial Meningitis | 0
Osteomyelitis / Septic Arthritis | 0
Bacterial Pneumonia | 0
Visceral Abscess | 0
Total | 0
Hospitalizations Secondary to Infection | 0
Mean Number of Validated Infections per Subject per Year | 0
p-value [The rate of validated infections was compared with a rate of 1 per subject per year, in accordance with recommendations by the FDA Blood Products Advisory Committee] | p < 0.0001
95% Confidence Interval | (0.000, 0.064)

The annualized rate of other prespecified validated bacterial infections (see Table 16), and the number of hospitalizations secondary to all validated infectious complications also were studied (see Table 15 and Table 16).

Table 16: Summary of Validated Other Bacterial Infections
 | Number of Events
Validated Infections [Other bacterial infections that met specific diagnostic requirements]
Urinary Tract Infection | 1
Gastroenteritis | 1
Lower Respiratory Tract Infection: Tracheobronchitis, Bronchiolitis (Without Evidence of Pneumonia) | 0
Lower Respiratory Tract Infection: Other Infections (e.g., Lung Abscess, Empyema) | 0
Otitis Media | 2
Total | 4
Hospitalizations Secondary to Infection | 0
Mean Number of Validated Infections per Subject per Year | 0.07
95% Confidence Interval | (0.018, 0.168)

None of the 61 treated subjects was positive for HCV, HIV-1, and HIV-2 and HBV prior to study entry and none converted from negative to positive during the 12-month period.

Treatment of Primary Immunodeficiency (Subcutaneous)

A prospective, open-label, non-controlled, multicenter study was conducted in the U.S. to determine the efficacy, tolerability and PK of GAMMAGARD LIQUID subcutaneous infusion in adult and pediatric subjects (N=49) with PI. All subjects were treated for 12 weeks with GAMMAGARD LIQUID intravenous infusion every 3 or 4 weeks. Subjects who were on intravenous treatment prior to entering the study were switched to GAMMAGARD LIQUID at the same dose and frequency. Subjects who were receiving subcutaneous immune globulin were switched to GAMMAGARD LIQUID at the intravenous dose they had received prior to switching to subcutaneous treatment. A PK analysis was performed at the end of the intravenous period in all subjects aged 12 years and older.

One week after the last intravenous infusion, each subject began subcutaneous treatment with GAMMAGARD LIQUID at 130% of the weekly equivalent of the intravenous dose for a minimum of 12 weeks. PK data from the first 15 adult subjects were used to determine the dose required to ensure that the IgG exposure with subcutaneous treatment was not inferior to that with intravenous treatment. The median dose determined from these subjects was 137% of the intravenous dose, and subsequently all subjects were treated for a minimum of 6 weeks at this dose. After 6 subcutaneous infusions, a trough IgG level was obtained and used to individually adapt the subcutaneous dose of GAMMAGARD LIQUID to compensate for individual variation from the mean value of 137% [see Pharmacokinetics (12.3) and Dosage and Administration (2.1)].

All subjects received a minimum of 12 infusions at this individually adapted dose and continued to receive subcutaneous treatment with GAMMAGARD LIQUID until the last subject completed the study. Subjects (N=47) were treated with 2,294 subcutaneous infusions of GAMMAGARD LIQUID: 4 subjects treated for up to 29 weeks, 17 subjects for 30 to 52 weeks, and 26 subjects for 53 weeks or longer. Two subjects that completed the intravenous treatment part of the study did not continue to the subcutaneous treatment part of the study. The median duration of subcutaneous treatment was 379 days (range: 57 to 477 days).

Efficacy was determined throughout the entire subcutaneous phase. There were 31 adults aged 16 years or older, 4 adolescents aged 12 to <16 years, and 14 children aged 2 to <12 years. The volume of GAMMAGARD LIQUID infused was 30 mL per site for subjects weighing 40 kg and greater, and 20 mL per site for those weighing less than 40 kg. The total weekly dose was divided by those values to determine the number of sites.

Mean weekly subcutaneous doses ranged from 181.9 mg/kg to 190.7 mg/kg (at 130% to 137% of the intravenous dose). In the study, the number of infusion sites per infusion was dependent on the dose of IgG and ranged from 2 to 10. In 75% of infusions, the number of infusion sites was 5 or fewer.

There were 3 serious validated bacterial infections, all bacterial pneumonia. None of these subjects required hospitalization to treat their infection. The annual rate of acute serious bacterial infections while on GAMMAGARD LIQUID subcutaneous treatment was 0.067, with an upper 99% confidence limit of 0.133, which is lower than the minimal goal of achieving a rate of <1 bacterial infection per patient-year.

Table 17 presents a summary of infections and associated events for subjects during subcutaneous treatment with GAMMAGARD LIQUID. The annual rate of any infection in this study during subcutaneous treatment, including viral and fungal infections, was 4.1 infections per subject per year.

Table 17: Summary of Infections and Associated Events
Number of subjects (efficacy phase); Total number of subject years; Annual rate of any infections | 47; 44; 4.1 (95% CI 3.2 to 5.1); infections/subject year
Antibiotic use [Included systemic and topical antibacterial, anti-fungal, anti-viral, and anti-protozoal antimicrobials] (prophylaxis or treatment)
Number of subjects (%); Annual rate | 40 (85.1%); 50.2 (95% CI 33.4 to 71.9); days/subject year
Days out of work/school/day care or unable to perform normal activities
Number of subjects (%); Annual rate | 25 (53.2%); 4.0 (95% CI 2.5 to 6.1); days/subject year
Hospitalizations due to infections
Number of subjects (%); Annual rate | 0 (0.0%); 0.0 (95% CI 0.0 to 0.1); days/subject year

Treatment of Multifocal Motor Neuropathy

A randomized, double-blind, placebo controlled, cross-over withdrawal study was conducted to evaluate the efficacy and safety/tolerability of GAMMAGARD LIQUID in adult subjects (N=44) with MMN.^12 The study examined grip strength in the more affected hand^11 (measured with dynamometer), and Guy's Neurological Disability Scale (GNDS) [upper limb part 6 subsection].^13 Study subjects were on a regimen of licensed immunoglobulin (existing maintenance dose ranging from 0.5 to 2.0 grams/kg/month) prior to enrollment and thus, the results cannot be generalized to naïve patients.

The study comprised of five study periods, each lasting 12 weeks: 3 stabilization phases, one randomized withdrawal phase and one cross-over phase. Open-label GAMMAGARD LIQUID was administered at the beginning (study period 1) and at the end of the study (study period 5) for clinical stabilization, and between the double-blinded periods to prevent carry-over effect (study period 3). If, during either of the double-blinded treatment periods, the subject's upper limb function involving the affected muscles deteriorated such that the subject had difficulty completing daily activities or experienced a decline in grip strength of ≥50% in the more affected hand, the subject was switched directly to the next stabilization phase of open-label GAMMAGARD LIQUID ("accelerated switch") without breaking the blind.

All subjects were treated for 12 weeks with open-label GAMMAGARD LIQUID during initial stabilization (study period 1). Each subject was then randomized in a double-blind manner to continuation of GAMMAGARD LIQUID or withdrawal of GAMMAGARD LIQUID and replacement by placebo for 12 weeks (study period 2); subjects who did not tolerate treatment were immediately transitioned to open label GAMMAGARD LIQUID. After infusion of open-label GAMMAGARD LIQUID for 12 weeks (study period 3), subjects crossed-over to receive placebo or GAMMAGARD LIQUID for 12 weeks (study period 4). No subject was allowed to experience placebo more than one time during the study. At study end, subjects were treated with open-label GAMMAGARD LIQUID for 12 weeks (study period 5).

Overall, 69% (n=29) of subjects required an accelerated switch to open-label treatment with GAMMAGARD LIQUID during the placebo period due to functional deterioration, but did not switch when receiving GAMMAGARD LIQUID. The median number of treatment days using GAMMAGARD LIQUID was 84 and the median number of days using placebo was 28. One subject (2.4%) switched to open‑label treatment during blinded GAMMAGARD LIQUID cross-over period 1, but did not switch during placebo administration (p <0.001).

Forty-four subjects were evaluated to demonstrate effectiveness of GAMMAGARD LIQUID to improve or maintain muscle strength and functional ability in patients with MMN.

Statistical significance (p<0.001) favoring GAMMAGARD LIQUID over placebo was demonstrated by a substantially lower decline from baseline (22.30%; 95% CI: 9.92% to 34.67%) in mean grip strength in the more affected hand following treatment (see Table 18). The difference in relative change for GAMMAGARD LIQUID and placebo of 22.94% (95% CI: 10.69 to 35.19).

Table 18: Relative Change in Grip Strength in the More Affected Hand during Cross-over Period (ANoVA) (mIntent-to-Treat Dataset) No. of subjects (N=41)
Statistics | Sequence 1 |  | Sequence 2 |  | Difference
Statistics | GAMMAGARD LIQUID | Placebo | Placebo | GAMMAGARD LIQUID | (GAMMAGARD LIQUID - Placebo)
N | 22 | 22 | 19 | 20 [A single subject in sequence 2, who was considered an outlier, was excluded from analysis] | 41
Mean (SD) | -16.36 (32.84) | -30.52 (29.68) | -29.19 (39.95) | 1.46 (10.72) | 22.30 (39.21)
Median | -3.90 | -27.00 | -25.03 | -0.11 | 26.6

Guy's Neurological Disability Scores (GNDS)^12 for the upper limbs, reflecting both fine motor skills and proximal strength, showed a significant difference in efficacy between GAMMAGARD LIQUID and placebo at the 2.5% level in favor of GAMMAGARD LIQUID. GNDS is a patient orientated clinical disability scale designed for multiple sclerosis and is considered appropriate for other neurological disorders.

As determined by GNDS scores for the upper limbs, 35.7% of subjects deteriorated while receiving placebo but not during treatment with GAMMAGARD LIQUID, whereas 11.9% of subjects deteriorated during GAMMAGARD LIQUID but not during the placebo period. This difference was statistically significant (p=0.021) (see Table 19). Overall, 4.8% of subjects showed deterioration with both placebo and GAMMAGARD LIQUID, while 47.6% showed no deterioration using either.

Table 19: McNemar’s Test for Subjects with Deterioration in Guy’s Neurological Disability Score (Intent-to-Treat Dataset) No. of subjects (N=42)
Deterioration on Placebo | 15 (35.7%)
Deterioration on GAMMAGARD LIQUID | 5 (11.9%)
Deterioration on both | 2 (4.8%)
No deterioration | 20 (47.6%)

When data from both treatment sequences were combined, a relative decline of ≥30% in grip strength in the more affected hand occurred in 42.9% of subjects during the placebo period, but not during treatment with GAMMAGARD LIQUID, whereas 4.8% of subjects experienced a ≥30% decline during treatment with GAMMAGARD LIQUID, but not during placebo. A relative decline of ≥30% in grip strength in the less affected hand occurred in 31.0% of subjects during the placebo period, but not during treatment with GAMMAGARD LIQUID. No subject experienced a ≥30% decline during treatment with GAMMAGARD LIQUID.

The Overall Disability Sum Score (ODSS) changed by -7.14% during placebo (indicating worsening of disability) and by -1.11% (indicating minimal change in disability) during treatment with GAMMAGARD LIQUID. For this specific analysis of ODSS, lower scores represented more disability.

With the dominant hand, subjects required 17% longer to complete the 9-hole peg test (a measure of dexterity) at the end of the placebo period, compared with baseline. By contrast, at the end of the GAMMAGARD LIQUID treatment period, subjects required 1.2% longer to complete the 9-hole peg test for the dominant hand compared with baseline. With the non-dominant hand, subjects required 33% longer to complete the 9-hole peg test at the end of the placebo period and 6.7% longer at the end of the GAMMAGARD LIQUID treatment period, compared with baseline.

Compared with baseline, assessment by subjects of physical functioning, as measured by visual analog scale (VAS) showed a mean change of 290% during placebo compared with baseline. Assessment by subjects of physical functioning showed a mean change of 73% during GAMMAGARD LIQUID treatment. Higher visual analog scale scores represent more severe disability.

Treatment of Chronic Inflammatory Demyelinating Polyneuropathy

In a prospective, open-label, single-arm, multicenter clinical study, a total of 18 subjects who developed a relapse in Epoch 1 and received GAMMAGARD LIQUID in Epoch 2 were included in efficacy analyses. GAMMAGARD LIQUID was administered at an induction dose of 2 g/kg body weight, followed by maintenance infusions at every 3 weeks for a period of 6 months. The dose of GAMMAGARD LIQUID treatment could be adjusted at the investigator's discretion. Adjustments to the dosing interval of every 3 weeks were not allowed. All subjects completed the study. All dosed subjects were analyzed for efficacy and safety.

Efficacy in Epoch 2 was based on responder rate, where a responder was defined as a subject who demonstrated an improvement of functional disability, indicated by at least a 1 point decrease in the adjusted Inflammatory Neuropathy Cause and Treatment (INCAT) disability score at the completion of the IV treatment period (6 months) or the last study visit of the IV treatment period, relative to pre-IV treatment baseline. The responder rate was 94.4% (N=18, 95% CI: 74.2% to 99.0%). The adjusted INCAT score returned back to baseline values prior to joining the study in 17 of the 18 subjects (94.4%) at 6 months. All subjects (N=18) had improvement in functional ability. Functional ability was a composite measure based on meeting any of the following criteria: decrease of ≥1 point in the adjusted INCAT disability score, increase of ≥8 kPa in hand grip strength in the more affected hand, or increase of ≥4 points in raw summed RODs score.

The mean adjusted INCAT score showed an improvement by 2.1 points. Medical Research Council (MRC) sum score improved by a mean of 5.4 points. The mean change in centile Rasch-built Overall Disability Scale (RODS) score was 15.0 points. Grip strength improved by a mean of 13.8 kPa in the more affected hand and 9.8 kPa in the less affected hand.

15 REFERENCES

1. Orange JS, Hossny EM, Weiler CR, Ballow M, Berger M, Bonilla FA, Buckley R, Chinen J, El-Gamal Y, Mazer BD, Nelson Jr. RP, Patel DD, Secord E, Sorenson RU, Wasserman RL, Cunningham-Rundles C, Use of Intravenous Immunoglobulin in Human Disease: A Review of Evidence by Members of the Primary Immunodeficiency Committee of the American Academy of Allergy, Asthma, and Immunology. J Allergy Clin Immunol 2006; 117:S525-53.
2. Bonilla FA, Bernstein IL, Khan DA, Ballas ZK, Chinen J, Frank MM, et al. Practice parameter for the diagnosis and management of primary immunodeficiency. Ann Allergy Asthma Immunol. 2005; 94(suppl 1):S1-63.
3. Pierce LR, Jain N. Risks associated with the use of intravenous immunoglobulin. Transfusion Med Rev. 2003;17:241-251.
4. Katz U, Sheonfeld Y. Review: intravenous immunoglobulin therapy and thromboembolic complications. Lupus 2005;14:802-8.
5. Wilson JR, Bhoopalam N, Fisher M. Hemolytic anemia associated with intravenous immunoglobulin. Muscle Nerve 1997;20:1142-1145.
6. Kessary-Shoham H, Levy Y, Shoenfeld Y, Lorber M, Gershon H. In vivo administration of intravenous immunoglobulin (IVIg) can lead to enhanced erythrocyte sequestration. J Autoimmun 1999;13:129-135.
7. Daw Z, Padmore R, Neurath D, Cober N, Tokessy M, Desjardins D, et al. Hemolytic transfusion reactions after administration of intravenous immune (gamma) globulin: a case series analysis. Transfusion. 2008; 48:1598-601.
8. Copelan EA, Strohm PL, Kennedy MS, Tuschka PJ, Hemolysis following intravenous immune globulin therapy. Transfusion 1986;26:410-412.
9. Kahwaji J, et al.; Acute hemolysis after High-Dose Intravenous Immunoglobin Therapy in Highly HLA Sensitized Patients. Clin J Am Soc Nephrol; 2009 (4):1993-97.
10. Kreil TR, Berting A, Kistner O, Kindermann J. West Nile virus and the safety of plasma derivatives: verification of high safety margins, and the validity of predictions based on model virus data. Transfusion 2003;43:1023-1028.
11. Shechtman O, Gestewitz L, Kimble C. Reliability and validity of the DynEx dynamometer. J. Hand Ther. 2005;18:339-347.
12. Hahn A., et al.; A controlled trial of intravenous immunoglobulin in multifocal motor neuropathy. Journal of the Peripheral Nervous System 2013; 18:321-330
13. Sharrack B, Hughes RA. The Guy's Neurological Disability Scale (GNDS): a new disability measure for multiple sclerosis. Mult. Scler. 1999;5:223-233.

16 HOW SUPPLIED/STORAGE AND HANDLING

GAMMAGARD LIQUID is supplied in single use bottles containing the labeled amount of functionally active IgG. The packaging of this product is not made with natural rubber latex.

The following presentations of GAMMAGARD LIQUID are available:

NDC Number | Volume | Grams Protein
0944-2700-02 | 10 mL | 1.0
0944-2700-03 | 25 mL | 2.5
0944-2700-04 | 50 mL | 5.0
0944-2700-05 | 100 mL | 10.0
0944-2700-06 | 200 mL | 20.0
0944-2700-07 | 300 mL | 30.0

- Do not freeze.
- Store GAMMAGARD LIQUID in the refrigerator or at room temperature.
- Refrigeration: 2° to 8°C [36° to 46°F] for up to 36 months.
- Room Temperature: up to 25°C [77°F] for up to 24 months.
- Expiration dates for both storage conditions are printed on the outer carton and vial label.
- Do not use past the applicable expiration date.

17 PATIENT COUNSELING INFORMATION

Advise the patient to read the FDA-approved patient labeling (Patient Information and Instructions for Use).

Inform patients to immediately report the following signs and symptoms to their healthcare provider:

- Decreased urine output, sudden weight gain, fluid retention/edema, and/or shortness of breath [see Warnings and Precautions (5.2)].
- Instruct patients to immediately report symptoms of thrombosis. These symptoms may include pain and/or swelling of an arm or leg with warmth over the affected area, discoloration of an arm or leg, unexplained shortness of breath, chest pain or discomfort that worsens on deep breathing, unexplained rapid pulse, numbness or weakness on one side of the body [see Warnings and Precautions (5.4)].
- Severe headache, neck stiffness, drowsiness, fever, sensitivity to light, painful eye movements, nausea, and vomiting [see Warnings and Precautions (5.5)].
- Increased heart rate, fatigue, yellowing of the skin or eyes, and dark-colored urine [see Warnings and Precautions (5.6)].
- Trouble breathing, chest pain, blue lips or extremities, or fever that can occur 1 to 6 hours after an infusion of GAMMAGARD LIQUID [see Warnings and Precautions (5.7)].

Prior to starting GAMMAGARD LIQUID ask about a history of IgA deficiency, allergic reactions to immune globulin or other blood products. Patients with a history of allergic reactions should not be treated subcutaneously at home until several treatments have been administered and tolerated under medical supervision.

Inform patients that GAMMAGARD LIQUID is made from human plasma and may contain infectious agents that can cause disease (e.g., viruses and, theoretically, the vCJD agent). The risk of GAMMAGARD LIQUID transmitting an infectious agent has been reduced by screening plasma donors for prior exposure, testing donated plasma, and inactivating or removing certain viruses during manufacturing. Patients should report any symptoms that concern them which might be caused by virus infections [see Warnings and Precautions (5.8)].

Inform patients that GAMMAGARD LIQUID can interfere with their immune response to live viral vaccines such as measles, mumps, rubella and varicella, and instruct patients to notify their healthcare professional of this potential interaction when they are receiving vaccinations [see Drug Interactions (7)].

Subcutaneous (SC) Administration Only

Self-administration – If self-administration is deemed to be appropriate by the physician, clear instructions and training on subcutaneous infusion should be given to the patient/caregiver, and the demonstration of their ability to independently administer subcutaneous infusions should be documented.

- Ensure the patient understands the importance of consistent weekly subcutaneous infusion to maintain appropriate steady IgG levels.
- Instruct the patient to keep a treatment diary/logbook. This diary/logbook should include information about each infusion such as, the time, date, dose, lot number(s) and any reactions.
- Inform the patient that mild to moderate local infusion-site reactions (e.g., swelling and redness) are a common side effect of subcutaneous treatment, but to contact their healthcare professional if a local reaction increases in severity or persists for more than a few days.

Manufactured by:

Takeda Pharmaceuticals U.S.A., Inc.
Cambridge, MA 02142
U.S. License No. 1898

GAMMAGARD LIQUID and GAMMAGARD are registered trademarks of Baxalta Incorporated.
TAKEDA and the are registered trademarks of Takeda Pharmaceutical Company Limited.

©2024 Takeda Pharmaceutical Company Limited. All rights reserved.

Revised: 9/2024
GLQ352

Patient Information
GAMMAGARD LIQUID®
Immune Globulin Infusion (Human) 10%
For Intravenous and Subcutaneous Administration

Information for Patients

The following summarizes important information about GAMMAGARD LIQUID. Please read it carefully before using this medicine. This information does not take the place of talking with your healthcare provider, and it does not include all of the important information about GAMMAGARD LIQUID. If you have any questions after reading this, ask your healthcare provider.

What is the most important information I need to know about GAMMAGARD LIQUID?

GAMMAGARD LIQUID can cause the following serious reactions:

- Severe allergic reactions causing difficulty in breathing or skin rashes
- Decreased kidney function or kidney failure
- Blood clots in the heart, brain, lungs or elsewhere in the body
- Severe headache, drowsiness, fever, painful eye movements, or nausea and vomiting
- Dark colored urine, swelling, fatigue, or difficulty breathing

What is GAMMAGARD LIQUID?

GAMMAGARD LIQUID is a ready-to-use, liquid medicine that contains immunoglobulin G (IgG) antibodies, which protect the body against infection. GAMMAGARD LIQUID is used to treat patients with primary immunodeficiency diseases (PI), patients with multifocal motor neuropathy (MMN) and patients with chronic inflammatory demyelinating polyneuropathy (CIDP).

There are many forms of PI. The most common types of PI result in an inability to make a very important type of protein called antibodies, which help the body fight off infections from bacteria or viruses. GAMMAGARD LIQUID is made from human plasma that is donated by healthy people. GAMMAGARD LIQUID contains antibodies collected from these healthy people that replace the missing antibodies in PI patients.

MMN is a rare disease that causes muscle weakness that worsens over time. It affects the strength of the lower parts of arms and hands more than the legs, usually without affecting the touch sensation.

CIDP is a rare disease. People who have CIDP are believed to have an autoimmune disease in which the body's immune system targets the nerves, leading to muscle weakness and numbness, usually in the arms and legs. IgG is thought to reduce the damage to the nerve and assist in defending the nerve from harm.

Who should not use GAMMAGARD LIQUID?

Do not use GAMMAGARD LIQUID if you have a known history of a severe allergic reaction to immune globulin or other blood products. If you have such a history, discuss this with your healthcare provider to determine if GAMMAGARD LIQUID can be given to you. Tell your healthcare provider if you have a condition called selective (or severe) immunoglobulin A (IgA) deficiency.

How should I use GAMMAGARD LIQUID?

GAMMAGARD LIQUID is given into a vein (intravenously) or under the skin (subcutaneously). For patients with PI, infusions into the vein are usually given every 3 or 4 weeks whereas infusions under the skin are given every week. For patients with MMN, infusions are given into a vein every 2 to 4 weeks as ordered by your physician. You and your healthcare provider will decide which way is best for you. Most of the time infusions under the skin are given at home by patients or caregivers. Although it is possible to give yourself infusions into the vein at home they are more often given in a hospital or infusion center by a nurse.

Instructions for giving GAMMAGARD LIQUID under the skin (subcutaneously) are provided in the Instructions for Use brochure. Only use GAMMAGARD LIQUID by yourself after you have been instructed by your healthcare provider.

What should I avoid while taking GAMMAGARD LIQUID?

GAMMAGARD LIQUID can make vaccines (like measles/mumps/rubella or chickenpox vaccines) not work as well for you. Before you get any vaccines, tell your healthcare provider that you take GAMMAGARD LIQUID.

Tell your healthcare provider if you are pregnant, or plan to become pregnant, or if you are nursing.

What are the possible or reasonably likely side effects of GAMMAGARD LIQUID?

The following one or more possible reactions may occur at the site of infusion. These generally go away within a few hours and are less likely after the first few infusions.

- Mild or moderate pain
- Swelling
- Itching

- Redness
- Bruising
- Warmth

During the infusion of GAMMAGARD LIQUID, look out for the first signs of the following common side effects:

- Headache
- Migraine
- Fever
- Fatigue
- Itching
- Rash/Hives
- Cough
- Chest pain/tightness
- Chills/Shaking chills
- Dizziness
- Nausea/Vomiting
- Faster Heart Rate

- Upper Abdominal Pain
- Increased Blood Pressure
- Muscle cramps
- Sore throat
- Anemia
- Illness
- Somnolence
- Tremor
- Nasal dryness
- Nasopharyngitis
- Pain in extremity

If any of the following problems occur after starting treatment with GAMMAGARD LIQUID, stop the infusion immediately and contact your healthcare provider or call emergency services. These could be signs of a serious problem.

- Hives, swelling in the mouth or throat, itching, trouble breathing, wheezing, fainting or dizziness. These could be signs of a serious allergic reaction.
- Bad headache with nausea, vomiting, stiff neck, fever, and sensitivity to light. These could be signs of irritation of the lining around your brain.
- Reduced urination, sudden weight gain, or swelling in your legs. These could be signs of a kidney problem.
- Pain, swelling, warmth, redness, or a lump in your legs or arms. These could be signs of a blood clot.
- Brown or red urine, fast heart rate, yellow skin or eyes. These could be signs of a liver problem or a blood problem.
- Chest pain or trouble breathing, or blue lips or extremities. These could be signs of a serious heart or lung problem.
- Fever over 100°F. This could be a sign of an infection.

These are not all of the possible side effects with GAMMAGARD LIQUID. You can ask your healthcare provider for physician's information leaflet. Tell your healthcare provider about any side effect that bothers you or that does not go away.

Whenever giving yourself treatments at home, you should have another responsible person present to help treat side effects or get help if you have a serious adverse reaction occur. Ask your healthcare provider whether you should have rescue medications, such as antihistamines or epinephrine.

How do I store GAMMAGARD LIQUID?

Store vials in their original boxes to protect from light. Do not freeze GAMMAGARD LIQUID.

You can store GAMMAGARD LIQUID in the refrigerator or at room temperature. The maximum storage time for GAMMAGARD LIQUID depends on the storage temperature you choose.

In the Refrigerator: at 2 to 8°C (36° to 46°F) for up to 36 months.

Room Temperature: up to 25°C (77°F) for up to 24 months.

The refrigerator and room temperature expiration dates are printed on the vial labels and the box. Always check the expiration date. You should not use the product after the expiration date.

Note: If you remove GAMMAGARD LIQUID from the refrigerator and store it at room temperature, do not refrigerate again.

Resources at Takeda Available to the Patients:

For more information on patient resources, education, or insurance assistance please visit www.immunedisease.com.

Detailed Instructions for Subcutaneous Administration for Patients with PI ONLY

Do not begin subcutaneous treatment with GAMMAGARD LIQUID® until you have received instructions as detailed above and are comfortable that you can perform all the steps on your own.

1. If refrigerated, remove GAMMAGARD LIQUID from refrigerator- remove the product box from the refrigerator and take the vial out of the box.

Allow vials to reach room temperature. This may take up to 60 minutes.

Do not heat up the product or shake the product.

If stored at room temperature, take the vial out of the box.

Check:

- Expiration date. Do not use beyond expiration date.
- Vial to see if it is clear and colorless to light yellow. If it is cloudy or has particles, do not use.
- Protective cap is on the vial. Do not use the product if it does not have the cap.

Repeat this step with as many boxes of GAMMAGARD LIQUID as necessary.

2. Gather all supplies – Collect all the items you will need for the infusion: vial(s) of GAMMAGARD LIQUID, infusion supplies (needle sets, transfer needles, alcohol swabs, syringes, gauze, and tape), sharps container, infusion pump, and treatment logbook.

3. Prepare a clean work area- Clean a work area with an antibacterial cleaner and place all gathered items on the clean surface. Find a quiet work area with as few distractions as possible.

4. Wash hands- Wash your hands thoroughly. Put on clean gloves if your health care provider has instructed you to wear them.

5. GAMMAGARD LIQUID preparation- If GAMMAGARD LIQUID is received in a bag or syringe, skip to step 7.

Remove the cap from the vial. Wipe the vial stopper with an alcohol swab and allow to air dry (at least 30 seconds).

6. Fill syringe from GAMMAGARD LIQUID vial(s) – Remove sterile syringe from package and attach to a sterile needle. Pull back on plunger of the syringe to fill it with air, which should equal the amount of liquid you will be taking from the vial. Insert needle into the center of the vial stopper. Inject air into the vial and withdraw GAMMAGARD LIQUID into the syringe. (Example: If withdrawing 50 mL of GAMMAGARD LIQUID, inject 50 mL of air into the vial).

If multiple vials are required to achieve the desired dose, repeat this step.

If using a vented spike, it is not necessary to inject air into the vial with the syringe. Attach a sterile syringe to the spike, insert the spike into the center of the stopper, and pull back on the plunger to withdraw the desired volume.

7. Prepare the infusion pump and tubing – If using a syringe driver pump, attach the syringe filled with GAMMAGARD LIQUID to the needle set. On a hard surface, gently push down on the plunger to fill (prime) the pump tubing up to the needle hub. This will ensure that no air is left in the tubing and needle (see picture).

If using a portable pump with GAMMAGARD LIQUID in a bag, follow manufacturer's instructions for preparing the pump and administration tubing, if needed.

8. Select the infusion sites - Select the number of infusion sites based on the volume of the total dose. It is recommended that you not inject more than 20 mL for children and 30 mL for adults into each infusion site.

See figure for potential locations of infusion sites (e.g., upper arms, abdomen, thighs, and lower back). Make sure sites are at least 2 inches apart. Avoid bony areas, visible blood vessels, scars and areas of inflammation (irritation) or infection.

9. Clean the infusion site(s)- Clean the infusion site(s) with an alcohol swab. Allow to dry (at least 30 seconds).

10. Insert the needle – Remove the needle cover. Firmly grasp skin and pinch at least one inch of skin between two fingers. Insert needle with a rapid motion straight into the skin at a 90 degree angle. Tape the needle in place. Repeat this step for each infusion site.

11. Check for proper needle placement – Before starting the infusion, check each needle for correct placement by gently pulling back on the attached syringe plunger and looking for any blood in the needle tubing. If you see any blood, remove and throw away the needle into the sharps container. Repeat filling (priming) and needle insertion steps in a different infusion site with a new needle.

12. Secure the needle to the skin and start infusion - Secure the needle(s) in place by putting a sterile clear bandage over the needle.

Follow the manufacturer's instructions to turn pump on. Check infusion sites occasionally throughout the infusion.

13. Remove needle set – After the infusion is complete, remove the needle set by pulling it straight out. Gently press a small piece of gauze over the needle site and cover with a protective dressing.

Throw away any unused product in the vial and the disposable supplies into the sharps container. Dispose of the sharps container using instructions provided with the container, or contact your healthcare provider.

14. Record the infusion - Remove the peel-off label from GAMMAGARD LIQUID vial, which has the product lot number and expiration date, and place the label in your treatment diary/logbook. Write down the date, time, dose, and any reactions after each infusion.

Manufactured by:

Takeda Pharmaceuticals U.S.A., Inc.
Cambridge, MA 02142
U.S. License No. 1898

GAMMAGARD LIQUID and GAMMAGARD are registered trademarks of Baxalta Incorporated.
TAKEDA and are registered trademarks of Takeda Pharmaceutical Company Limited.

©2024 Takeda Pharmaceutical Company Limited. All rights reserved.

Revised: 9/2024
GLQ352

PRINCIPAL DISPLAY PANEL - 10 mL Bottle Label

NDC 0944-2700-08
Single-dose container

Immune Globulin Infusion
(Human) 10%
GAMMAGARD LIQUID®

1g
10mL

Solution for Infusion

For Intravenous or Subcutaneous Use.
Not made with natural rubber latex.

Rx Only

Takeda Pharmaceuticals U.S.A., Inc.
Cambridge, MA 02142
U.S. License No. 1898

LE-07-62516

Takeda

PRINCIPAL DISPLAY PANEL - 10 mL Bottle Carton

NDC 0944-2700-02

Single-dose container

Immune Globulin Infusion
(Human) 10%
GAMMAGARD LIQUID®

1g
10mL

Solution for Infusion

For Intravenous or Subcutaneous
Administration

Rx Only

Takeda

PRINCIPAL DISPLAY PANEL - 25 mL Bottle Label

NDC 0944-2700-09
Single-dose container

Immune Globulin Infusion
(Human) 10%
GAMMAGARD LIQUID®

2.5g
25mL

Solution for Infusion

For Intravenous or Subcutaneous Use.
Not made with natural rubber latex.

Rx Only

Takeda Pharmaceuticals U.S.A., Inc.
Cambridge, MA 02142
U.S. License No. 1898

LE-07-62520

Takeda

PRINCIPAL DISPLAY PANEL - 25 mL Bottle Carton

NDC 0944-2700-03

Single-dose container

Immune Globulin Infusion
(Human) 10%
GAMMAGARD LIQUID®

2.5g
25mL

Solution for Infusion

For Intravenous or Subcutaneous
Administration

Rx Only

Takeda

PRINCIPAL DISPLAY PANEL - 50 mL Bottle Label

NDC 0944-2700-10
Single-dose container

Immune Globulin Infusion
(Human) 10%
GAMMAGARD LIQUID®

5g
50mL

Solution for Infusion

For Intravenous or Subcutaneous Administration.
Not made with natural rubber latex.
Refrigeration: 2°-8°C (36°F-46°F). Do not freeze.
Room temperature: up to 25°C (77°F).

Rx Only

Takeda Pharmaceuticals U.S.A., Inc.
Cambridge, MA 02142
U.S. License No. 1898

LE-07-62522

Takeda

PRINCIPAL DISPLAY PANEL - 50 mL Bottle Carton

NDC 0944-2700-04

Single-dose container

Immune Globulin Infusion
(Human) 10%
GAMMAGARD LIQUID®

5g
50mL

Solution for Infusion

For Intravenous or Subcutaneous
Administration

Rx Only

Takeda

PRINCIPAL DISPLAY PANEL - 100 mL Bottle Label

NDC 0944-2700-11
Single-dose container

Immune Globulin Infusion
(Human) 10%
GAMMAGARD LIQUID®

10g
100mL

Solution for Infusion

For Intravenous or Subcutaneous Administration.
Not made with natural rubber latex.
Refrigeration: 2°-8°C (36°F-46°F). Do not freeze.
Room temperature: up to 25°C (77°F).

Rx Only

Takeda Pharmaceuticals U.S.A., Inc.
Cambridge, MA 02142
U.S. License No. 1898

LE-07-62524

Takeda

PRINCIPAL DISPLAY PANEL - 100 mL Bottle Carton

NDC 0944-2700-05

Single-dose container

Immune Globulin Infusion
(Human) 10%
GAMMAGARD LIQUID®

10g
100mL

Solution for
Infusion

For Intravenous or
Subcutaneous Administration

Rx Only

Takeda

PRINCIPAL DISPLAY PANEL - 200 mL Bottle Label

NDC 0944-2700-12
Single-dose container

Immune Globulin Infusion
(Human) 10%
GAMMAGARD LIQUID®

20g
200mL

Solution for Infusion

For Intravenous or Subcutaneous Administration.
Not made with natural rubber latex.
Refrigeration: 2°-8°C (36°F-46°F). Do not freeze.
Room temperature: up to 25°C (77°F).

Rx Only

Takeda Pharmaceuticals U.S.A., Inc.
Cambridge, MA 02142
U.S. License No. 1898

LE-07-62526

Takeda

PRINCIPAL DISPLAY PANEL - 200 mL Bottle Carton

NDC 0944-2700-06

Single-dose container

Immune Globulin Infusion
(Human) 10%
GAMMAGARD LIQUID®

20g
200mL

Solution for Infusion

For Intravenous or Subcutaneous
Administration

Rx Only

Takeda

PRINCIPAL DISPLAY PANEL - 300 mL Bottle Label

NDC 0944-2700-13
Single-dose container

Immune Globulin Infusion
(Human) 10%
GAMMAGARD LIQUID®

30g
300mL

Solution for Infusion

For Intravenous or Subcutaneous Administration.
Not made with natural rubber latex.
Refrigeration: 2°-8°C (36°F-46°F). Do not freeze.
Room temperature: up to 25°C (77°F).

Rx Only

Takeda Pharmaceuticals U.S.A., Inc.
Cambridge, MA 02142
U.S. License No. 1898

LE-07-62528

Takeda

PRINCIPAL DISPLAY PANEL - 300 mL Bottle Carton

NDC 0944-2700-07

Single-dose container

Immune Globulin Infusion
(Human) 10%
GAMMAGARD LIQUID®

30g
300mL

Solution for Infusion

For Intravenous or
Subcutaneous Administration

Rx Only

Takeda